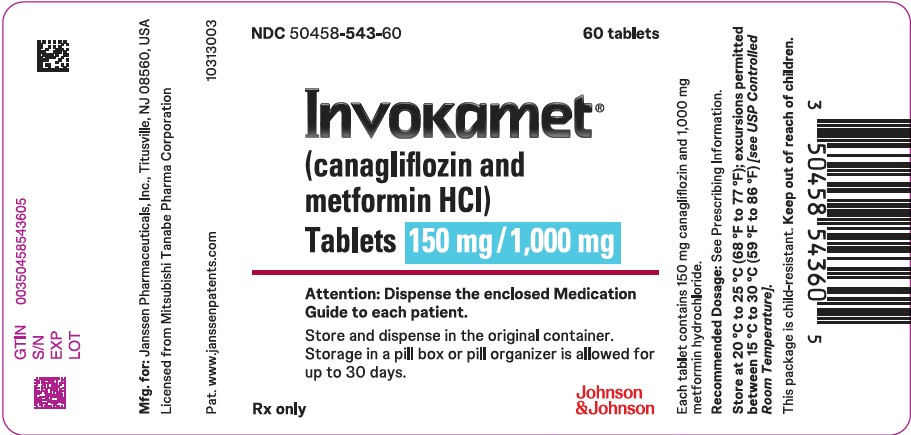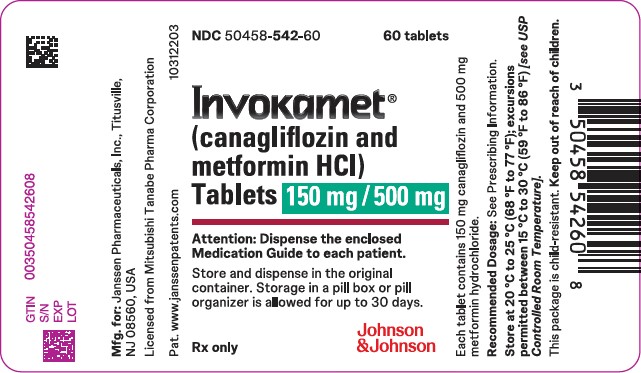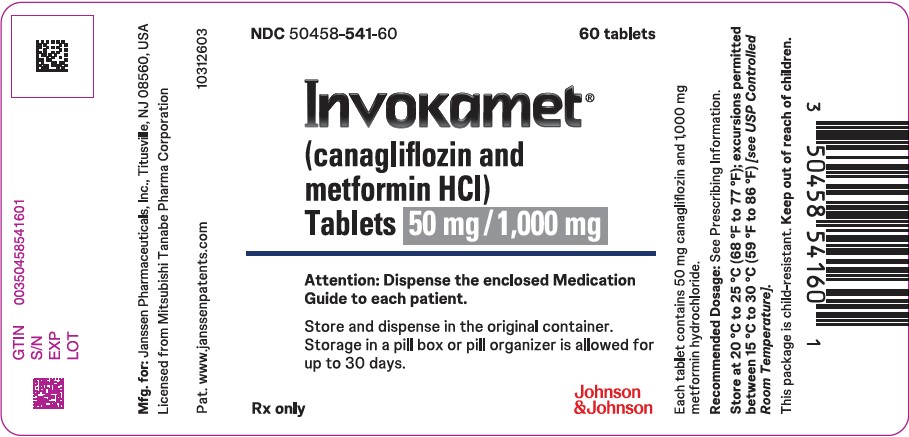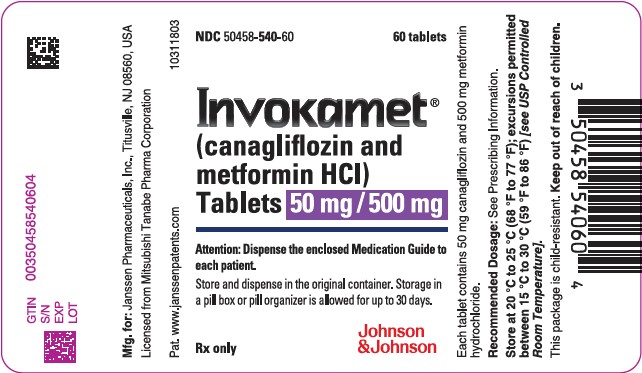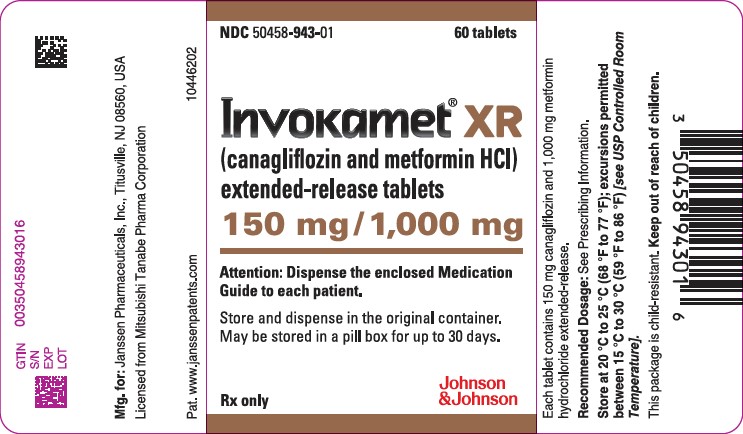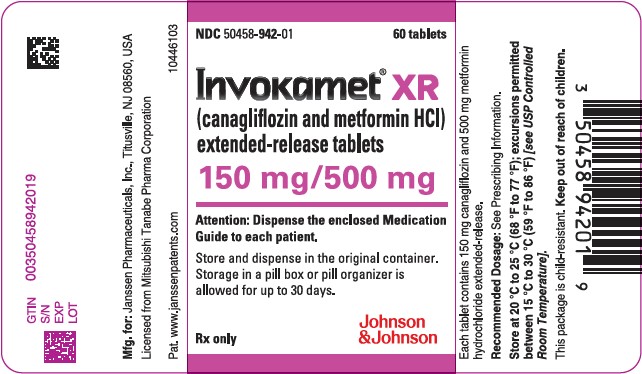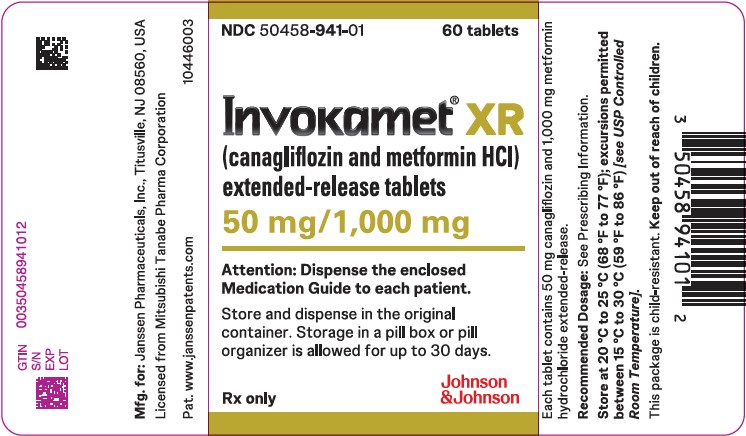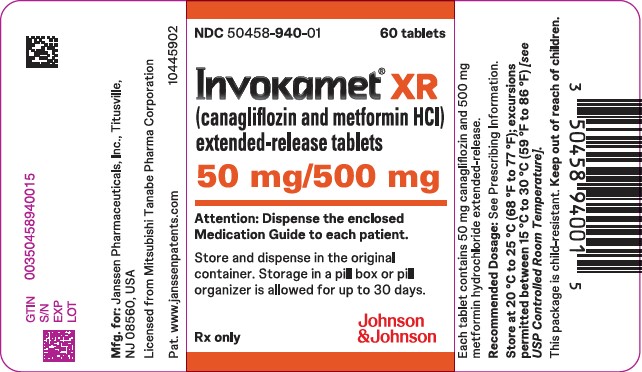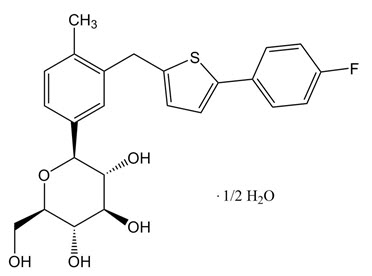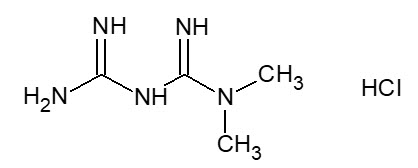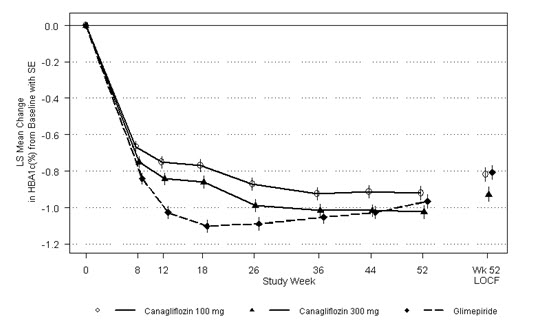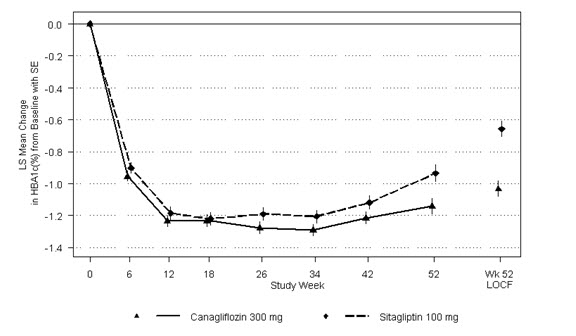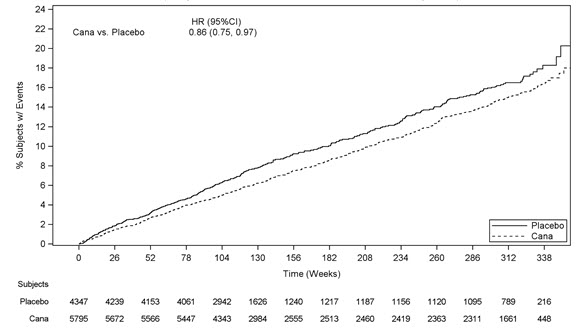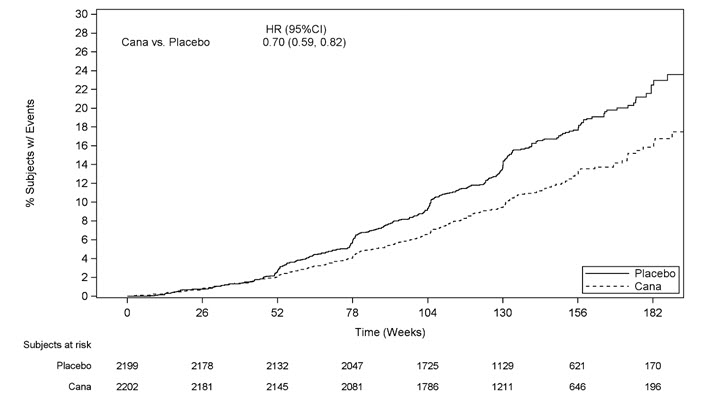 DRUG LABEL: INVOKAMET
NDC: 50458-540 | Form: TABLET, FILM COATED
Manufacturer: Janssen Pharmaceuticals, Inc.
Category: prescription | Type: HUMAN PRESCRIPTION DRUG LABEL
Date: 20250821

ACTIVE INGREDIENTS: CANAGLIFLOZIN 50 mg/1 1; METFORMIN HYDROCHLORIDE 500 mg/1 1
INACTIVE INGREDIENTS: CROSCARMELLOSE SODIUM; HYPROMELLOSE, UNSPECIFIED; MAGNESIUM STEARATE; MICROCRYSTALLINE CELLULOSE; WATER; POLYETHYLENE GLYCOL 3350; POLYVINYL ALCOHOL, UNSPECIFIED; TALC; TITANIUM DIOXIDE

HIGHLIGHTS OF PRESCRIBING INFORMATION

These highlights do not include all the information needed to use INVOKAMET or INVOKAMET XR safely and effectively. See full prescribing information for INVOKAMET or INVOKAMET XR.
INVOKAMET®(canagliflozin and metformin hydrochloride) tablets, for oral use
INVOKAMET®XR (canagliflozin and metformin hydrochloride) extended-release tablets, for oral use
Initial U.S. Approval: 2014

WARNING: LACTIC ACIDOSIS

See full prescribing information for complete boxed warning.

- Postmarketing cases of metformin-associated lactic acidosis have resulted in death, hypothermia, hypotension, and resistant bradyarrhythmias. Symptoms included malaise, myalgias, respiratory distress, somnolence, and abdominal pain. Laboratory abnormalities included elevated blood lactate levels, anion gap acidosis, increased lactate/pyruvate ratio; and metformin plasma levels generally >5 mcg/mL. (5.1)
- Risk factors include renal impairment, concomitant use of certain drugs, age >65 years old, radiological studies with contrast, surgery and other procedures, hypoxic states, excessive alcohol intake, and hepatic impairment. Steps to reduce the risk of and manage metformin-associated lactic acidosis in these high risk groups are provided in the Full Prescribing Information. (5.1)
- If lactic acidosis is suspected, discontinue INVOKAMET or INVOKAMET XR and institute general supportive measures in a hospital setting. Prompt hemodialysis is recommended. (5.1)

RECENT MAJOR CHANGES

Indications and Usage (1) | 12/2024
Dosage and Administration (2.2, 2.3, 2.4) | 12/2024
Dosage and Administration (2.6) | 08/2024
Warnings and Precautions (5.3) | 01/2024

1 INDICATIONS AND USAGE

INVOKAMET and INVOKAMET XRare a combination of canagliflozin, a sodium-glucose co-transporter 2 (SGLT2) inhibitor, and metformin hydrochloride (HCl), a biguanide, indicated as an adjunct to diet and exercise to improve glycemic control in adults and pediatric patients aged 10 years and older with type 2 diabetes mellitus (1).

Canagliflozin

Canagliflozin, when used as a component of INVOKAMET or INVOKAMET XR is indicated in adults with type 2 diabetes mellitus to reduce the risk of:

- Major adverse cardiovascular events in adults with type 2 diabetes mellitus and established cardiovascular disease (1).
- End-stage kidney disease, doubling of serum creatinine, cardiovascular death, and hospitalization for heart failure in adults with type 2 diabetes mellitus and diabetic nephropathy with albuminuria (1).

Limitations of Use:

Not recommended for use to improve glycemic control in patients with type 1 diabetes mellitus (1).

2 DOSAGE AND ADMINISTRATION

- Assess renal function before initiating and as clinically indicated. Assess volume status and correct volume depletion before initiating (2.1).
- Individualize starting dose based on the patient's current regimen and renal function. See Table 1in the full prescribing information for recommended starting dosages based on the current regimen (2.2, 2.3).
- The maximum recommended total daily dosage is 300 mg of canagliflozin and 2,000 mg of metformin HCl (2.2).
- Initiation of INVOKAMET or INVOKAMET XR is not recommended in patients with an eGFR less than 45 mL/min/1.73 m^2, due to the metformin HCl component (2.3).
- INVOKAMET: take one tablet orally twice daily with meals (2.2).
- INVOKAMET XR: take two tablets orally once daily with the morning meal. Swallow whole. Never crush, cut, or chew (2.2).
- Gradually escalate the dosage of metformin HCl in INVOKAMET or INVOKAMET XR to reduce the risk of gastrointestinal adverse reactions with metformin HCl (2.2).
- Dose adjustment for patients with renal impairment may be required (2.3).
- See full prescribing information for INVOKAMET and INVOKAMET XR dosage modifications due to drug interactions (2.4).
- May need to be discontinued at time of, or prior to, iodinated contrast imaging procedures (2.5).
- Withhold INVOKAMET or INVOKAMET XR at least 3 days, if possible, prior to surgery or procedures associated with prolonged fasting (2.6).

3 DOSAGE FORMS AND STRENGTHS

INVOKAMET tablets:

- Canagliflozin 50 mg and metformin HCl 500 mg (3)
- Canagliflozin 50 mg and metformin HCl 1,000 mg (3)
- Canagliflozin 150 mg and metformin HCl 500 mg (3)
- Canagliflozin 150 mg and metformin HCl 1,000 mg (3)

INVOKAMET XR extended-release tablets:

- Canagliflozin 50 mg and metformin HCl 500 mg (3)
- Canagliflozin 50 mg and metformin HCl 1,000 mg (3)
- Canagliflozin 150 mg and metformin HCl 500 mg (3)
- Canagliflozin 150 mg and metformin HCl 1,000 mg (3)

4 CONTRAINDICATIONS

- Severe renal impairment (eGFR less than 30 mL/min/1.73 m^2) (4)
- Metabolic acidosis, including diabetic ketoacidosis (4)
- Serious hypersensitivity reaction to canagliflozin or metformin HCl (4)

5 WARNINGS AND PRECAUTIONS

- Diabetic Ketoacidosis in Patients with Type 1 Diabetes Mellitus and Other Ketoacidosis: Consider ketone monitoring in patients at risk for ketoacidosis, as indicated. Assess for ketoacidosis regardless of presenting blood glucose levels and discontinue INVOKAMET or INVOKAMET XR if ketoacidosis is suspected. Monitor patients for resolution of ketoacidosis before restarting (5.2).
- Lower Limb Amputation: Monitor patients for infection or ulcers of lower limb and discontinue if these occur (5.3).
- Volume Depletion: May result in acute kidney injury. Before initiating, assess and correct volume status in patients with renal impairment, elderly patients, or patients on loop diuretics. Monitor for signs and symptoms during therapy (5.4).
- Urosepsis and Pyelonephritis: Evaluate patients for signs and symptoms of urinary tract infections and treat promptly, if indicated (5.5).
- Hypoglycemia with Concomitant Use with Insulin or Insulin Secretagogues: Consider a lower dose of insulin or insulin secretagogue to reduce the risk of hypoglycemia when used in combination (5.6).
- Necrotizing Fasciitis of the Perineum (Fournier's Gangrene): Serious, life-threatening cases have occurred in both females and males. Assess patients presenting with pain or tenderness, erythema, or swelling in the genital or perineal area, along with fever or malaise. If suspected, institute prompt treatment (5.7).
- Genital Mycotic Infections: Monitor and treat if indicated (5.8).
- Hypersensitivity Reactions: Discontinue and monitor until signs and symptoms resolve (5.9).
- Bone Fracture: Consider factors that contribute to fracture risk before initiating INVOKAMET or INVOKAMET XR (5.10).
- Vitamin B12Deficiency : Metformin HCl may lower vitamin B12levels. Measure hematological parameters annually and vitamin B12at 2- to 3-year intervals and manage any abnormalities (5.11).

6 ADVERSE REACTIONS

- Most common adverse reactions associated with canagliflozin (5% or greater incidence): female genital mycotic infections, urinary tract infection, and increased urination (6.1).
- Most common adverse reactions associated with metformin HCl (5% or greater incidence) are diarrhea, nausea, vomiting, flatulence, asthenia, indigestion, abdominal discomfort, and headache (6.1).

To report SUSPECTED ADVERSE REACTIONS, contact Janssen Pharmaceuticals, Inc. at 1-800-526-7736 or FDA at 1-800-FDA-1088 or www.fda.gov/medwatch.

7 DRUG INTERACTIONS

- Carbonic Anhydrase Inhibitors:May increase risk of lactic acidosis. Consider more frequent monitoring (7)
- Drugs that Reduce Metformin Clearance:May increase risk of lactic acidosis. Consider benefits and risks of concomitant use (7)
- See full prescribing information for additional drug interactions and information on interference of INVOKAMET and INVOKAMET XR with laboratory tests. (7)

8 USE IN SPECIFIC POPULATIONS

- Pregnancy: Advise females of the potential risk to a fetus especially during the second and third trimesters (8.1)
- Lactation: Not recommended when breastfeeding (8.2)
- Females and Males of Reproductive Potential: Advise premenopausal females of the potential for an unintended pregnancy (8.3)
- Geriatrics: Higher incidence of adverse reactions related to reduced intravascular volume. Assess renal function more frequently (8.5)
- Renal Impairment: Higher incidence of adverse reactions related to hypotension and renal function (8.6)
- Hepatic Impairment: Avoid use in patients with hepatic impairment (8.7)

FULL PRESCRIBING INFORMATION

WARNING: LACTIC ACIDOSIS

- Post-marketing cases of metformin-associated lactic acidosis have resulted in death, hypothermia, hypotension, and resistant bradyarrhythmias. The onset of metformin-associated lactic acidosis is often subtle, accompanied only by nonspecific symptoms such as malaise, myalgias, respiratory distress, somnolence, and abdominal pain. Metformin-associated lactic acidosis was characterized by elevated blood lactate levels (> 5 mmol/Liter), anion gap acidosis (without evidence of ketonuria or ketonemia), an increased lactate/pyruvate ratio; and metformin plasma levels generally >5 mcg/mL [see Warnings and Precautions (5.1)] .
- Risk factors for metformin-associated lactic acidosis include renal impairment, concomitant use of certain drugs (e.g., carbonic anhydrase inhibitors such as topiramate), age 65 years old or greater, having a radiological study with contrast, surgery and other procedures, hypoxic states (e.g., acute congestive heart failure), excessive alcohol intake, and hepatic impairment [see Warnings and Precautions (5.1)] .
- Steps to reduce the risk of and manage metformin-associated lactic acidosis in these high risk groups are provided in the full prescribing information [see Dosage and Administration (2.2, 2.3), Contraindications (4), Warnings and Precautions (5.1), Drug Interactions (7), and Use in Specific Populations (8.6, 8.7)] .
- If metformin-associated lactic acidosis is suspected, immediately discontinue INVOKAMET or INVOKAMET XR and institute general supportive measures in a hospital setting. Prompt hemodialysis is recommended [see Warnings and Precautions (5.1)] .

1 INDICATIONS AND USAGE

INVOKAMET

INVOKAMET is a combination of canagliflozin and metformin HCl immediate-release indicated as an adjunct to diet and exercise to improve glycemic control in adults and pediatric patients aged 10 years and older with type 2 diabetes mellitus.

INVOKAMET XR

INVOKAMET XR is a combination of canagliflozin and metformin HCl extended-release indicated as an adjunct to diet and exercise to improve glycemic control in adults and pediatric patients aged 10 years and older with type 2 diabetes mellitus.

Canagliflozin

Canagliflozin, when used as a component of INVOKAMET or INVOKAMET XR, is indicated in adults with type 2 diabetes mellitus to reduce the risk of:

- Major adverse cardiovascular events (cardiovascular death, nonfatal myocardial infarction and nonfatal stroke) in adults with type 2 diabetes mellitus and established cardiovascular disease (CVD).
- End-stage kidney disease (ESKD), doubling of serum creatinine, cardiovascular (CV) death, and hospitalization for heart failure in adults with type 2 diabetes mellitus and diabetic nephropathy with albuminuria greater than 300 mg/day.

Limitations of Use

INVOKAMET or INVOKAMET XR are not recommended for use to improve glycemic control in patients with type 1 diabetes mellitus [see Warnings and Precautions (5.2)] .

2 DOSAGE AND ADMINISTRATION

2.1 Prior to Initiation of INVOKAMET or INVOKAMET XR

Assess renal function before initiating INVOKAMET or INVOKAMET XR and as clinically indicated [see Dosage and Administration (2.3), Contraindications (4), and Warnings and Precautions (5.1, 5.4)].

In patients with volume depletion, correct this condition before initiating INVOKAMET or INVOKAMET XR [see Warnings and Precautions (5.4)and Use in Specific Populations (8.5, 8.6)] .

2.2 Recommended Dosage and Administration

INVOKAMET and INVOKAMET XR

- INVOKAMET and INVOKAMET XR contain canagliflozin and metformin HCl. For the available strengths of the canagliflozin and metformin HCl components in INVOKAMET and INVOKAMET XR, see Dosage Forms and Strengths (3).
- Individualize the starting dosage of INVOKAMET or INVOKAMET XR based on the patient's current regimen as presented in Table 1 and based on renal function as presented in Table 2 [see Dosage and Administration (2.3] .

INVOKAMET

Take one tablet of INVOKAMET orally twice daily with meals.

INVOKAMET XR

Take two tablets of INVOKAMET XR orally once daily with the morning meal. Swallow each tablet whole and never crush, cut, or chew.

Table 1 presents the recommended starting dosage of INVOKAMET and INVOKAMET XR based on the patient's current regimen.

Table 1: Recommended Starting Dosage Based on the Current Regimen
Current Regimen | INVOKAMET Recommended Dosage | INVOKAMET XR Recommended Dosage
Not treated with either canagliflozin or metformin HCl | Total daily dosage is canagliflozin 100 mg and metformin HCl 1,000 mg
Metformin HCl [For patients taking an evening dosage of metformin HCl extended-release tablets, skip the last dose before starting INVOKAMET or INVOKAMET XR the following morning.] | Total daily dosage is canagliflozin 100 mg and the nearest appropriate total daily dosage of metformin HCl
Canagliflozin | The same total daily dosage of canagliflozin and a total daily dosage of metformin HCl 1,000 mg
Canagliflozin and metformin HCl | The same total daily dosage of canagliflozin and the nearest appropriate total daily dosage of metformin HCl

Recommended Dosage for Additional Glycemic Control in Adults and Pediatric Patients Aged 10 Years and Older

INVOKAMET

The dosage of canagliflozin in INVOKAMET may be increased to the maximum total daily dosage of 300 mg (150 mg orally twice daily) in patients tolerating a dosage of 100 mg (50 mg twice daily) of canagliflozin.

The dosage of metformin HCl in INVOKAMET may be increased to the maximum total daily dosage of 2,000 mg (1,000 mg orally twice daily), with gradual escalation to reduce the risk of gastrointestinal adverse reactions with metformin HCl [see Adverse Reactions (6.1)].

INVOKAMET XR

The dosage of canagliflozin in INVOKAMET XR may be increased to the maximum total daily dosage of 300 mg orally once daily in patients tolerating a 100 mg once daily dosage of canagliflozin.

The dosage of metformin HCl in INVOKAMET XR may be increased to the maximum total daily dosage of 2,000 mg once daily, with gradual escalation to reduce the risk of gastrointestinal adverse reactions with metformin HCl [see Adverse Reactions (6.1)].

2.3 Recommended Dosage in Adults and Pediatric Patients Aged 10 Years and Older with Renal Impairment

- Initiation of INVOKAMET or INVOKAMET XR is not recommended in adults or pediatric patients aged 10 years and older with an eGFR less than 45 mL/min/1.73 m^2, due to the metformin component.
- Table 2 provides dosage recommendations for adults and pediatric patients aged 10 years and older with renal impairment, based on eGFR [see Use in Specific Populations (8.6)and Clinical Studies (14.4)].

Table 2: Recommended Dosage in Adults and Pediatric Patients Aged 10 Years and Older with Renal Impairment
Estimated Glomerular Filtration Rate [eGFR (mL/min/1.73 m^2)] | Recommended Dosage of INVOKAMET or INVOKAMET XR [For the dosing frequency of INVOKAMET and INVOKAMET XR, see Dosage and Administration (2.2).]
eGFR 45 to less than 60 | The maximum total daily dosage of canagliflozin is 100 mg.
eGFR 30 to less than 45 | Assess the benefit risk of continuing INVOKAMET or INVOKAMET XR. The maximum total daily dosage of canagliflozin is 100 mg.
eGFR less than 30 | Contraindicated. If eGFR falls below 30 during treatment; discontinue INVOKAMET or INVOKAMET XR [see Contraindications (4)] .

2.4 Concomitant Use with UDP-Glucuronosyltransferase (UGT) Enzyme Inducers

When co-administering INVOKAMET or INVOKAMET XR with an inducer of UGT (e.g., rifampin, phenytoin, phenobarbital, ritonavir), increase the total daily dosage of canagliflozin based on renal function [see Drug Interactions (7)] :

- In patients with eGFR 60 mL/min/1.73 m^2or greater, increase the total daily dosage of canagliflozin to 200 mg in patients currently tolerating a total daily dosage of canagliflozin 100 mg. The maximum total daily dosage of canagliflozin is 300 mg.
- In patients with eGFR less than 60 mL/min/1.73 m^2, increase the total daily dosage of canagliflozin to a maximum of 200 mg in patients currently tolerating a total daily dosage of canagliflozin 100 mg.

2.5 Discontinuation for Iodinated Contrast Imaging Procedures

Discontinue INVOKAMET or INVOKAMET XR at the time of, or prior to, an iodinated contrast imaging procedure in patients with an eGFR of less than 60 mL/min/1.73 m^2; in patients with a history of liver disease, alcoholism or heart failure; or in patients who will be administered intra-arterial iodinated contrast. Re-evaluate eGFR 48 hours after the imaging procedure; restart INVOKAMET or INVOKAMET XR if renal function is stable [see Warnings and Precautions (5.1)] .

2.6 Temporary Interruption for Surgery

Withhold INVOKAMET or INVOKAMET XR at least 3 days, if possible, prior to surgery or procedures associated with prolonged fasting. Resume INVOKAMET or INVOKAMET XR when the patient is clinically stable and has resumed oral intake [see Warnings and Precautions (5.2)and Clinical Pharmacology (12.2)].

3 DOSAGE FORMS AND STRENGTHS

INVOKAMET (canagliflozin and metformin HCl) tablets are available as follows:

Canagliflozin Strength | Metformin HCl Strength | Color/Shape | Tablet Identifiers [Embossing appears on both sides of tablet.]
50 mg | 500 mg | white/capsule-shaped | CM 155
50 mg | 1,000 mg | beige/capsule-shaped | CM 551
150 mg | 500 mg | yellow/capsule-shaped | CM 215
150 mg | 1,000 mg | purple/capsule-shaped | CM 611

INVOKAMET XR (canagliflozin and metformin HCl) extended-release tablets are available as follows:

Canagliflozin Strength | Metformin HCl Strength | Color/Shape | Tablet Identifiers [Embossing appears on one side only of tablet.]
50 mg | 500 mg | almost white to light orange/oblong, biconvex | CM1
50 mg | 1,000 mg | pink/oblong, biconvex | CM3
150 mg | 500 mg | orange/oblong, biconvex | CM2
150 mg | 1,000 mg | reddish brown/oblong, biconvex | CM4

4 CONTRAINDICATIONS

INVOKAMET or INVOKAMET XR is contraindicated in patients with:

- Severe renal impairment (eGFR less than 30 mL/min/1.73 m^2) [see Warnings and Precautions (5.1)and Use in Specific Populations (8.6)] .
- Acute or chronic metabolic acidosis, including diabetic ketoacidosis [see Warnings and Precautions (5.2)] .
- Serious hypersensitivity reaction to canagliflozin or metformin HCl, such as anaphylaxis or angioedema [see Warnings and Precautions (5.9)and Adverse Reactions (6)] .

5 WARNINGS AND PRECAUTIONS

5.1 Lactic Acidosis

There have been post-marketing cases of metformin-associated lactic acidosis, including fatal cases. These cases had a subtle onset and were accompanied by nonspecific symptoms such as malaise, myalgias, abdominal pain, respiratory distress, or increased somnolence; however, hypothermia, hypotension and resistant bradyarrhythmias have occurred with severe acidosis. Metformin-associated lactic acidosis was characterized by elevated blood lactate concentrations (>5 mmol/Liter), anion gap acidosis (without evidence of ketonuria or ketonemia), and an increased lactate:pyruvate ratio; metformin plasma levels generally >5 mcg/mL. Metformin decreases liver uptake of lactate increasing lactate blood levels which may increase the risk of lactic acidosis, especially in patients at risk.

If metformin-associated lactic acidosis is suspected, general supportive measures should be instituted promptly in a hospital setting, along with immediate discontinuation of INVOKAMET or INVOKAMET XR. In INVOKAMET or INVOKAMET XR-treated patients with a diagnosis or strong suspicion of lactic acidosis, prompt hemodialysis is recommended to correct the acidosis and remove accumulated metformin (metformin is dialyzable, with a clearance of up to 170 mL/min under good hemodynamic conditions). Hemodialysis has often resulted in reversal of symptoms and recovery.

Educate patients and their families about the symptoms of lactic acidosis and if these symptoms occur instruct them to discontinue INVOKAMET or INVOKAMET XR and report these symptoms to their healthcare provider.

For each of the known and possible risk factors for metformin-associated lactic acidosis, recommendations to reduce the risk of and manage metformin-associated lactic acidosis are provided below:

Renal Impairment:The postmarketing metformin-associated lactic acidosis cases primarily occurred in patients with significant renal impairment. The risk of metformin accumulation and metformin-associated lactic acidosis increases with the severity of renal impairment because metformin is substantially excreted by the kidney. Clinical recommendations based upon the patient's renal function include [see Dosage and Administration (2.4)and Clinical Pharmacology (12.3)].

- Before initiating INVOKAMET or INVOKAMET XR, obtain an estimated glomerular filtration rate (eGFR).
- INVOKAMET or INVOKAMET XR is contraindicated in patients with an eGFR less than 30 mL/min/1.73 m^2 [see Contraindications (4)] .
- Obtain an eGFR at least annually in all patients taking INVOKAMET or INVOKAMET XR. In patients at increased risk for the development of renal impairment (e.g., the elderly), renal function should be assessed more frequently.

Drug Interactions:The concomitant use of INVOKAMET or INVOKAMET XR with specific drugs may increase the risk of metformin-associated lactic acidosis: those that impair renal function, result in significant hemodynamic change, interfere with acid-base balance or increase metformin accumulation (e.g. cationic drugs) [see Drug Interactions (7)]. Therefore, consider more frequent monitoring of patients.

Age 65 or Greater:The risk of metformin-associated lactic acidosis increases with the patient's age because elderly patients have a greater likelihood of having hepatic, renal, or cardiac impairment than younger patients. Assess renal function more frequently in elderly patients [see Use in Specific Populations (8.5)].

Radiological Studies with Contrast:Administration of intravascular iodinated contrast agents in metformin-treated patients has led to an acute decrease in renal function and the occurrence of lactic acidosis. Stop INVOKAMET or INVOKAMET XR at the time of, or prior to, an iodinated contrast imaging procedure in patients with an eGFR less than 60 mL/min/1.73 m^2; in patients with a history of hepatic impairment, alcoholism, or heart failure; or in patients who will be administered intra-arterial iodinated contrast. Re-evaluate eGFR 48 hours after the imaging procedure, and restart INVOKAMET or INVOKAMET XR if renal function is stable.

Surgery and Other Procedures:Withholding of food and fluids during surgical or other procedures may increase the risk for volume depletion, hypotension and renal impairment.

INVOKAMET or INVOKAMET XR should be temporarily discontinued while patients have restricted food and fluid intake.

Hypoxic States:Several of the postmarketing cases of metformin-associated lactic acidosis occurred in the setting of acute congestive heart failure (particularly when accompanied by hypoperfusion and hypoxemia). Cardiovascular collapse (shock), acute myocardial infarction, sepsis, and other conditions associated with hypoxemia have been associated with lactic acidosis and may also cause pre-renal azotemia. When such events occur, discontinue INVOKAMET or INVOKAMET XR.

Excessive Alcohol Intake:Alcohol potentiates the effect of metformin on lactate metabolism and this may increase the risk of metformin-associated lactic acidosis. Warn patients against excessive alcohol intake while receiving INVOKAMET or INVOKAMET XR.

Hepatic Impairment:Patients with hepatic impairment have developed metformin-associated lactic acidosis. This may be due to impaired lactate clearance resulting in higher lactate blood levels. Therefore, avoid use of INVOKAMET or INVOKAMET XR in patients with clinical or laboratory evidence of hepatic disease.

5.2 Diabetic Ketoacidosis in Patients with Type 1 Diabetes Mellitus and Other Ketoacidosis

In patients with type 1 diabetes mellitus, INVOKAMET or INVOKAMET XR significantly increases the risk of diabetic ketoacidosis, a life-threatening event, beyond the background rate. In placebo-controlled trials of patients with type 1 diabetes mellitus, the risk of ketoacidosis was markedly increased in patients who received sodium glucose transporter 2 (SGLT2) inhibitors compared to patients who received placebo; this risk may be greater with higher doses of INVOKAMET or INVOKAMET XR. INVOKAMET or INVOKAMET XR is not indicated for glycemic control in patients with type 1 diabetes mellitus.

Type 2 diabetes mellitus and pancreatic disorders (e.g., history of pancreatitis or pancreatic surgery) are also risk factors for ketoacidosis. There have been postmarketing reports of fatal events of ketoacidosis in patients with type 2 diabetes mellitus using SGLT2 inhibitors, including INVOKAMET or INVOKAMET XR.

Precipitating conditions for diabetic ketoacidosis or other ketoacidosis include under-insulinization due to insulin dose reduction or missed insulin doses, acute febrile illness, reduced caloric intake, ketogenic diet, surgery, volume depletion, and alcohol abuse.

Signs and symptoms are consistent with dehydration and severe metabolic acidosis and include nausea, vomiting, abdominal pain, generalized malaise, and shortness of breath. Blood glucose levels at presentation may be below those typically expected for diabetic ketoacidosis (e.g., less than 250 mg/dL). Ketoacidosis and glucosuria may persist longer than typically expected. Urinary glucose excretion persists for 3 days after discontinuing INVOKAMET or INVOKAMET XR [see Clinical Pharmacology (12.2)] ; however, there have been postmarketing reports of ketoacidosis and/or glucosuria lasting greater than 6 days and some up to 2 weeks after discontinuation of SGLT2 inhibitors.

Consider ketone monitoring in patients at risk for ketoacidosis if indicated by the clinical situation. Assess for ketoacidosis regardless of presenting blood glucose levels in patients who present with signs and symptoms consistent with severe metabolic acidosis. If ketoacidosis is suspected, discontinue INVOKAMET or INVOKAMET XR, promptly evaluate, and treat ketoacidosis, if confirmed. Monitor patients for resolution of ketoacidosis before restarting INVOKAMET or INVOKAMET XR.

Withhold INVOKAMET or INVOKAMET XR, if possible, in temporary clinical situations that could predispose patients to ketoacidosis. Resume INVOKAMET or INVOKAMET XR when the patient is clinically stable and has resumed oral intake [see Dosage and Administration (2.7)].

Educate all patients on the signs and symptoms of ketoacidosis and instruct patients to discontinue INVOKAMET or INVOKAMET XR and seek medical attention immediately if signs and symptoms occur.

5.3 Lower Limb Amputation

An increased risk of lower limb amputations associated with canagliflozin, a component of INVOKAMET or INVOKAMET XR, versus placebo was observed in CANVAS (5.9 vs 2.8 events per 1,000 patient-years) and CANVAS-R (7.5 vs 4.2 events per 1,000 patient-years), two randomized, placebo-controlled trials evaluating adult patients with type 2 diabetes who had either established cardiovascular disease or were at risk for cardiovascular disease. The risk of lower limb amputations was observed at both the 100 mg and 300 mg once daily dosage regimens. The amputation data for CANVAS and CANVAS-R are shown in Tables 4 and 5, respectively [see Adverse Reactions (6.1)] .

Amputations of the toe and midfoot (99 out of 140 patients with amputations receiving canagliflozin in the two trials) were the most frequent; however, amputations involving the leg, below and above the knee, were also observed (41 out of 140 patients with amputations receiving canagliflozin in the two trials). Some patients had multiple amputations, some involving both lower limbs.

Lower limb infections, gangrene, and diabetic foot ulcers were the most common precipitating medical events leading to the need for an amputation. The risk of amputation was highest in patients with a baseline history of prior amputation, peripheral vascular disease, and neuropathy.

Counsel patients about the importance of routine preventative foot care. Monitor patients receiving INVOKAMET or INVOKAMET XR for signs and symptoms of infection (including osteomyelitis), new pain or tenderness, sores or ulcers involving the lower limbs, and discontinue INVOKAMET or INVOKAMET XR if these complications occur.

5.4 Volume Depletion

Canagliflozin can cause intravascular volume contraction which may sometimes manifest as symptomatic hypotension or acute transient changes in creatinine [see Adverse Reactions (6.1)] . There have been post-marketing reports of acute kidney injury which are likely related to volume depletion, some requiring hospitalizations and dialysis, in patients with type 2 diabetes mellitus receiving SGLT2 inhibitors, including canagliflozin. Patients with impaired renal function (eGFR less than 60 mL/min/1.73 m^2), elderly patients, or patients on loop diuretics may be at increased risk for volume depletion or hypotension. Before initiating INVOKAMET or INVOKAMET XR in patients with one or more of these characteristics, assess and correct volume status. Monitor for signs and symptoms of volume depletion after initiating therapy.

5.5 Urosepsis and Pyelonephritis

There have been postmarketing reports of serious urinary tract infections including urosepsis and pyelonephritis requiring hospitalization in patients receiving canagliflozin. Treatment with INVOKAMET or INVOKAMET XR increases the risk for urinary tract infections. Evaluate patients for signs and symptoms of urinary tract infections and treat promptly, if indicated [see Adverse Reactions (6)] .

5.6 Hypoglycemia with Concomitant Use with Insulin or Insulin Secretagogues

Insulin and insulin secretagogues are known to cause hypoglycemia. INVOKAMET or INVOKAMET XR may increase the risk of hypoglycemia when combined with insulin or an insulin secretagogue [see Adverse Reactions (6.1)] . The risk of hypoglycemia may be lowered by a reduction in the dose of sulfonylurea (or other concomitantly administered insulin secretagogues) or insulin. Inform patients using these concomitant medications of the risk of hypoglycemia and educate them on the signs and symptoms of hypoglycemia.

5.7 Necrotizing Fasciitis of the Perineum (Fournier's Gangrene)

Reports of necrotizing fasciitis of the perineum (Fournier's gangrene), a rare but serious and life-threatening necrotizing infection requiring urgent surgical intervention, have been identified in postmarketing surveillance in patients with diabetes mellitus receiving SGLT2 inhibitors, including canagliflozin. Cases have been reported in both females and males. Serious outcomes have included hospitalization, multiple surgeries, and death.

Patients treated with INVOKAMET or INVOKAMET XR presenting with pain or tenderness, erythema, or swelling in the genital or perineal area, along with fever or malaise, should be assessed for necrotizing fasciitis. If suspected, start treatment immediately with broad-spectrum antibiotics and, if necessary, surgical debridement. Discontinue INVOKAMET or INVOKAMET XR, closely monitor blood glucose levels, and provide appropriate alternative therapy for glycemic control.

5.8 Genital Mycotic Infections

Canagliflozin increases the risk of genital mycotic infections. Patients with a history of genital mycotic infections and uncircumcised males were more likely to develop genital mycotic infections [see Adverse Reactions (6.1)] . Monitor and treat appropriately.

5.9 Hypersensitivity Reactions

Hypersensitivity reactions, including angioedema and anaphylaxis, have been reported with canagliflozin. These reactions generally occurred within hours to days after initiating canagliflozin. If hypersensitivity reactions occur, discontinue use of INVOKAMET or INVOKAMET XR; treat and monitor until signs and symptoms resolve [see Contraindications (4)and Adverse Reactions (6.1, 6.2)] .

5.10 Bone Fracture

An increased risk of bone fracture, occurring as early as 12 weeks after treatment initiation, was observed in adult patients using canagliflozin in the CANVAS trial [see Clinical Studies (14.3)] . Consider factors that contribute to fracture risk prior to initiating INVOKAMET or INVOKAMET XR [see Adverse Reactions (6.1)] .

5.11 Vitamin B12Levels

In metformin HCl clinical trials of 29-week duration, a decrease to subnormal levels of previously normal serum vitamin B12levels was observed in approximately 7% of patients. Such decrease, possibly due to interference with B12absorption from the B12-intrinsic factor complex, may be associated with anemia but appears to be rapidly reversible with discontinuation of metformin HCl or vitamin B12supplementation. Certain individuals (those with inadequate vitamin B12or calcium intake or absorption) appear to be predisposed to developing subnormal vitamin B12levels. Measure hematologic parameters on an annual basis and vitamin B12at 2- to 3-year intervals in patients on INVOKAMET or INVOKAMET XR and manage any abnormalities [see Adverse Reactions (6.1)].

6 ADVERSE REACTIONS

The following important adverse reactions are also discussed elsewhere in the labeling:

- Lactic Acidosis [see Boxed Warningand Warnings and Precautions (5.1, 5.4)]
- Diabetic Ketoacidosis in Patients with Type 1 Diabetes and Other Ketoacidosis [see Warnings and Precautions (5.2)]
- Lower Limb Amputation [see Warnings and Precautions (5.3)]
- Volume Depletion [see Warnings and Precautions (5.4)]
- Urosepsis and Pyelonephritis [see Warnings and Precautions (5.5)]
- Hypoglycemia with Concomitant Use with Insulin or Insulin Secretagogues [see Warnings and Precautions (5.6)]
- Necrotizing Fasciitis of the Perineum (Fournier's gangrene) [see Warnings and Precautions (5.7)]
- Genital Mycotic Infections [see Warnings and Precautions (5.8)]
- Hypersensitivity Reactions [see Warnings and Precautions (5.9)]
- Bone Fracture [see Warnings and Precautions (5.10)]
- Vitamin B12Deficiency [see Warnings and Precautions (5.11)]

6.1 Clinical Studies Experience

Because clinical trials are conducted under widely varying conditions, adverse reaction rates observed in the clinical trials of a drug cannot be directly compared to the rates in the clinical trials of another drug and may not reflect the rates observed in clinical practice.

Canagliflozin has been evaluated in clinical trials in adults and pediatric patients aged 10 years and older with type 2 diabetes mellitus. Additionally, canagliflozin has been studied in clinical trials in adult patients with type 2 diabetes mellitus who also have heart failure or chronic kidney disease. The overall safety profile of canagliflozin was consistent across the studied indications.

Clinical Trials in Adults with Type 2 Diabetes Mellitus

Pool of Placebo-Controlled Trials for Glycemic Control

Canagliflozin

The data in Table 3 are derived from four 26-week placebo-controlled trials where canagliflozin was used as monotherapy in one trial and as add-on therapy in three trials. These data reflect exposure of 1,667 adult patients to canagliflozin and a mean duration of exposure to canagliflozin of 24 weeks with 1,275 patients exposed to a combination of canagliflozin and metformin HCl. Patients received canagliflozin 100 mg (N=833), canagliflozin 300 mg (N=834) or placebo (N=646) once daily. The mean daily dose of metformin HCl was 2,138 mg (SD 337.3) for the 1,275 patients in the three placebo-controlled metformin HCl add-on trials. The mean age of the population was 56 years and 2% were older than 75 years of age. Fifty percent (50%) of the population was male and 72% were White, 12% were Asian, and 5% were Black or African American. At baseline the population had diabetes for an average of 7.3 years, had a mean HbA1Cof 8.0% and 20% had established microvascular complications of diabetes. Baseline renal function was normal or mildly impaired (mean eGFR 88 mL/min/1.73 m^2).

Table 3 shows common adverse reactions associated with the use of canagliflozin. These adverse reactions were not present at baseline, occurred more commonly on canagliflozin than on placebo, and occurred in at least 2% of patients treated with either canagliflozin 100 mg or canagliflozin 300 mg.

Table 3: Adverse Reactions from Pool of Four 26−Week Placebo-Controlled Trials Reported in ≥ 2% of Canagliflozin-Treated Adult Patients [The four placebo-controlled trials included one monotherapy trial and three add-on combination trials with metformin HCl, metformin HCl and sulfonylurea, or metformin HCl and pioglitazone.]
Adverse Reaction | Placebo N=646 | Canagliflozin 100 mg N=833 | Canagliflozin 300 mg N=834
Urinary tract infections [Urinary tract infections include the following adverse reactions: Urinary tract infection, Cystitis, Kidney infection, and Urosepsis.] | 3.8% | 5.9% | 4.4%
Increased urination [Increased urination includes the following adverse reactions: Polyuria, Pollakiuria, Urine output increased, Micturition urgency, and Nocturia.] | 0.7% | 5.1% | 4.6%
Thirst [Thirst includes the following adverse reactions: Thirst, Dry mouth, and Polydipsia.] | 0.1% | 2.8% | 2.4%
Constipation | 0.9% | 1.8% | 2.4%
Nausea | 1.6% | 2.1% | 2.3%
 | N=312 | N=425 | N=430
Female genital mycotic infections [Female genital mycotic infections include the following adverse reactions: Vulvovaginal candidiasis, Vulvovaginal mycotic infection, Vulvovaginitis, Vaginal infection, Vulvitis, and Genital infection fungal.] | 2.8% | 10.6% | 11.6%
Vulvovaginal pruritus | 0.0% | 1.6% | 3.2%
 | N=334 | N=408 | N=404
Male genital mycotic infections [Male genital mycotic infections include the following adverse reactions: Balanitis or Balanoposthitis, Balanitis candida, and Genital infection fungal.] | 0.7% | 4.2% | 3.8%
Note: Percentages were weighted by trials. Trial weights were proportional to the harmonic mean of the three treatment sample sizes.

Abdominal pain was also more commonly reported in patients taking canagliflozin 100 mg (1.8%), 300 mg (1.7%) than in patients taking placebo (0.8%).

Canagliflozin and Metformin HCl

The incidence and type of adverse reactions in the three 26-week placebo-controlled metformin HCl tablets add-on trials in adults, representing a majority of data from the four 26-week placebo-controlled trials, was similar to the adverse reactions described in Table 3. There were no additional adverse reactions identified in the pooling of these three placebo-controlled trials that included metformin HCl tablets relative to the four placebo-controlled trials.

In a trial in adults with canagliflozin as initial combination therapy with metformin HCl [see Clinical Studies (14.1)] , an increased incidence of diarrhea was observed in the canagliflozin and metformin HCl combination groups (4.2%) compared to canagliflozin or metformin HCl monotherapy groups (1.7%).

Placebo-Controlled Trial in Diabetic Nephropathy

The occurrence of adverse reactions for canagliflozin was evaluated in patients participating in CREDENCE, a trial in adult patients with type 2 diabetes mellitus and diabetic nephropathy with albuminuria ˃ 300 mg/day [see Clinical Studies (14.4)] . These data reflect exposure of 2,201 adult patients to canagliflozin and a mean duration of exposure to canagliflozin of 137 weeks.

The rate of lower limb amputations associated with the use of canagliflozin 100 mg relative to placebo was 12.3 vs 11.2 events per 1,000 patient-years, respectively, with 2.6 years mean duration of follow-up.

The incidence of hypotension was 2.8% and 1.5% on canagliflozin 100 mg and placebo, respectively.

Pool of Placebo- and Active-Controlled Trials for Glycemic Control and Cardiovascular Outcomes

The occurrence of adverse reactions for canagliflozin was evaluated in adult patients participating in placebo- and active-controlled trials and in an integrated analysis of two cardiovascular trials, CANVAS and CANVAS-R.

The types and frequency of common adverse reactions observed in the pool of eight clinical trials (which reflect an exposure of 6,177 adult patients to canagliflozin) were consistent with those listed in Table 3. Percentages were weighted by trials. Trial weights were proportional to the harmonic mean of the three treatment sample sizes. In this pool, canagliflozin was also associated with the adverse reactions of fatigue (1.8%, 2.2%, and 2.0% with comparator, canagliflozin 100 mg, and canagliflozin 300 mg, respectively) and loss of strength or energy (i.e., asthenia) (0.6%, 0.7%, and 1.1% with comparator, canagliflozin 100 mg, and canagliflozin 300 mg, respectively).

In the pool of eight clinical trials, the incidence rate of pancreatitis (acute or chronic) was 0.1%, 0.2%, and 0.1% receiving comparator, canagliflozin 100 mg, and canagliflozin 300 mg, respectively.

In the pool of eight clinical trials, hypersensitivity-related adverse reactions (including erythema, rash, pruritus, urticaria, and angioedema) was 3.0%, 3.8%, and 4.2% of adult patients receiving comparator, canagliflozin 100 mg, and canagliflozin 300 mg, respectively. Five patients experienced serious adverse reactions of hypersensitivity with canagliflozin, which included 4 patients with urticaria and 1 patient with a diffuse rash and urticaria occurring within hours of exposure to canagliflozin. Among these patients, 2 patients discontinued canagliflozin. One patient with urticaria had recurrence when canagliflozin was re-initiated.

Photosensitivity-related adverse reactions (including photosensitivity reaction, polymorphic light eruption, and sunburn) occurred in 0.1%, 0.2%, and 0.2% of patients receiving comparator, canagliflozin 100 mg, and canagliflozin 300 mg, respectively.

Other adverse reactions occurring more frequently on canagliflozin than on comparator were:

Lower Limb Amputation

An increased risk of lower limb amputations associated with canagliflozin was observed in CANVAS (5.9 vs 2.8 events per 1,000 patient-years) and CANVAS-R (7.5 vs 4.2 events per 1,000 patient-years), two randomized, placebo-controlled trials evaluating adult patients with type 2 diabetes who had either established cardiovascular disease or were at risk for cardiovascular disease. Patients in CANVAS and CANVAS-R were followed for an average of 5.7 and 2.1 years, respectively [see Clinical Studies (14.3)] . The amputation data for CANVAS and CANVAS-R are shown in Tables 4 and 5, respectively .

Table 4: Amputations in the CANVAS Trial in Adults with Type 2 Diabetes Mellitus and Atherosclerotic Cardiovascular Disease
 | Placebo N=1,441 | Canagliflozin 100 mg N=1,445 | Canagliflozin 300 mg N=1,441 | Canagliflozin (Pooled) N=2,886
Patients with an amputation, n (%) | 22 (1.5) | 50 (3.5) | 45 (3.1) | 95 (3.3)
Total amputations | 33 | 83 | 79 | 162
Amputation incidence rate (per 1,000 patient-years) | 2.8 | 6.2 | 5.5 | 5.9
Hazard Ratio (95% CI) | -- | 2.24 (1.36, 3.69) | 2.01 (1.20, 3.34) | 2.12 (1.34, 3.38)
Note: Incidence is based on the number of patients with at least one amputation, and not the total number of amputation events. A patient's follow-up is calculated from Day 1 to the first amputation event date. Some patients had more than one amputation.

Table 5: Amputations in the CANVAS-R Trial in Adults with Type 2 Diabetes Mellitus and Atherosclerotic Cardiovascular Disease
 | Placebo N=2,903 | Canagliflozin 100 mg (with up-titration to 300 mg) N=2,904
Patients with an amputation, n (%) | 25 (0.9) | 45 (1.5)
Total amputations | 36 | 59
Amputation incidence rate (per 1,000 patient-years) | 4.2 | 7.5
Hazard Ratio (95% CI) | -- | 1.80 (1.10, 2.93)
Note: Incidence is based on the number of patients with at least one amputation, and not the total number of amputation events. A patient's follow-up is calculated from Day 1 to the first amputation event date. Some patients had more than one amputation.

Renal Cell Carcinoma

In the CANVAS trial in adults (mean duration of follow-up of 5.7 years) [see Clinical Studies (14.3)] , the incidence of renal cell carcinoma was 0.15% (2/1,331) and 0.29% (8/2,716) for placebo and canagliflozin, respectively, excluding patients with less than 6 months of follow-up, less than 90 days of treatment, or a history of renal cell carcinoma. A causal relationship to canagliflozin could not be established due to the limited number of cases.

Volume Depletion-Related Adverse Reactions

Canagliflozin results in an osmotic diuresis, which may lead to reductions in intravascular volume. In clinical trials for glycemic control, treatment with canagliflozin was associated with a dose-dependent increase in the incidence of volume depletion-related adverse reactions (e.g., hypotension, postural dizziness, orthostatic hypotension, syncope, and dehydration). An increased incidence was observed in adult patients on the 300 mg dose. The three factors associated with the largest increase in volume depletion-related adverse reactions in these trials were the use of loop diuretics, moderate renal impairment (eGFR 30 to less than 60 mL/min/1.73 m^2), and age 75 years and older (Table 6) [see Use in Specific Populations (8.5and 8.6)] .

Table 6: Adult Patients with at Least One Volume Depletion-Related Adverse Reaction (Pooled Results from 8 Clinical Trials for Glycemic Control)
Baseline Characteristic | Comparator Group [Includes placebo and active-comparator groups] % | Canagliflozin 100 mg % | Canagliflozin 300 mg %
Overall population | 1.5% | 2.3% | 3.4%
75 years of age and older [Patients could have more than 1 of the listed risk factors] | 2.6% | 4.9% | 8.7%
eGFR less than 60 mL/min/1.73 m^2 | 2.5% | 4.7% | 8.1%
Use of loop diuretic | 4.7% | 3.2% | 8.8%

Falls

In a pool of nine clinical trials in adults with mean duration of exposure to canagliflozin of 85 weeks, the proportion of patients who experienced falls was 1.3%, 1.5%, and 2.1% with comparator, canagliflozin 100 mg, and canagliflozin 300 mg, respectively. The higher risk of falls for patients treated with canagliflozin was observed within the first few weeks of treatment.

Genital Mycotic Infections

In the pool of four placebo-controlled clinical trials in adults for glycemic control, female genital mycotic infections (e.g., vulvovaginal mycotic infection, vulvovaginal candidiasis, and vulvovaginitis) occurred in 2.8%, 10.6%, and 11.6% of females treated with placebo, canagliflozin 100 mg, and canagliflozin 300 mg, respectively. Patients with a history of genital mycotic infections were more likely to develop genital mycotic infections on canagliflozin. Female patients who developed genital mycotic infections on canagliflozin were more likely to experience recurrence and require treatment with oral or topical antifungal agents and anti-microbial agents. In females, discontinuation due to genital mycotic infections occurred in 0% and 0.7% of patients treated with placebo and canagliflozin, respectively.

In the pool of four placebo-controlled clinical trials in adults, male genital mycotic infections (e.g., candidal balanitis, balanoposthitis) occurred in 0.7%, 4.2%, and 3.8% of males treated with placebo, canagliflozin 100 mg, and canagliflozin 300 mg, respectively. Male genital mycotic infections occurred more commonly in uncircumcised males and in males with a prior history of balanitis or balanoposthitis. Male patients who developed genital mycotic infections on canagliflozin were more likely to experience recurrent infections (22% on canagliflozin versus none on placebo) and require treatment with oral or topical antifungal agents and anti-microbial agents than patients on comparators. In males, discontinuations due to genital mycotic infections occurred in 0% and 0.5% of patients treated with placebo and canagliflozin, respectively.

In the pooled analysis of 8 randomized trials in adults evaluating glycemic control, phimosis was reported in 0.3% of uncircumcised male patients treated with canagliflozin and 0.2% required circumcision to treat the phimosis.

Hypoglycemia

In canagliflozin glycemic control trials, hypoglycemia was defined as any event regardless of symptoms, where biochemical hypoglycemia was documented (any glucose value below or equal to 70 mg/dL). Severe hypoglycemia was defined as an event consistent with hypoglycemia where the patient required the assistance of another person to recover, lost consciousness, or experienced a seizure (regardless of whether biochemical documentation of a low glucose value was obtained). In individual clinical trials of glycemic control in adults [see Clinical Studies (14.1)] , episodes of hypoglycemia occurred at a higher rate when canagliflozin was co-administered with insulin or sulfonylureas (Table 7).

Table 7: Incidence of Hypoglycemia [Number of patients experiencing at least one event of hypoglycemia based on either biochemically documented episodes or severe hypoglycemic events in the intent-to-treat population] in Randomized Clinical Trials of Glycemic Control in Adults
Monotherapy (26 weeks) | Placebo (N=192) | Canagliflozin 100 mg (N=195) | Canagliflozin 300 mg (N=197)
Overall [N (%)] | 5 (2.6) | 7 (3.6) | 6 (3.0)
In Combination with Metformin HCl (26 weeks) | Placebo + Metformin HCl (N=183) | Canagliflozin 100 mg + Metformin HCl (N=368) | Canagliflozin 300 mg + Metformin HCl (N=367)
Overall [N (%)] | 3 (1.6) | 16 (4.3) | 17 (4.6)
Severe [N (%)] [Severe episodes of hypoglycemia were defined as those where the patient required the assistance of another person to recover, lost consciousness, or experienced a seizure (regardless of whether biochemical documentation of a low glucose value was obtained)] | 0 (0) | 1 (0.3) | 1 (0.3)
In Combination with Metformin HCl (18 weeks) [Phase 2 clinical trial with twice daily dosing (50 mg or 150 mg twice daily in combination with metformin HCl)] | Placebo (N=93) | Canagliflozin 100 mg (N=93) | Canagliflozin 300 mg (N=93)
Overall [N (%)] | 3 (3.2) | 4 (4.3) | 3 (3.2)
In Combination with Metformin HCl + Sulfonylurea (26 weeks) | Placebo + Metformin HCl + Sulfonylurea (N=156) | Canagliflozin 100 mg + Metformin HCl + Sulfonylurea (N=157) | Canagliflozin 300 mg + Metformin HCl + Sulfonylurea (N=156)
Overall [N (%)] | 24 (15.4) | 43 (27.4) | 47 (30.1)
Severe [N (%)] | 1 (0.6) | 1 (0.6) | 0
In Combination with Metformin HCl + Pioglitazone (26 weeks) | Placebo + Metformin HCl + Pioglitazone (N=115) | Canagliflozin 100 mg + Metformin HCl + Pioglitazone (N=113) | Canagliflozin 300 mg + Metformin HCl + Pioglitazone (N=114)
Overall [N (%)] | 3 (2.6) | 3 (2.7) | 6 (5.3)
In Combination with Insulin (18 weeks) | Placebo (N=565) | Canagliflozin 100 mg (N=566) | Canagliflozin 300 mg (N=587)
Overall [N (%)] | 208 (36.8) | 279 (49.3) | 285 (48.6)
Severe [N (%)] | 14 (2.5) | 10 (1.8) | 16 (2.7)
In Combination with Insulin and Metformin HCl (18 weeks) [Subgroup of patients (N=287) from insulin subtrial on canagliflozin in combination with metformin HCl and insulin (with or without other antiglycemic agents)] | Placebo (N=145) | Canagliflozin 100 mg (N=139) | Canagliflozin 300 mg (N=148)
Overall [N (%)] | 66 (45.5) | 58 (41.7) | 70 (47.3)
Severe [N (%)] | 4 (2.8) | 1 (0.7) | 3 (2.0)

Bone Fracture

In the CANVAS trial in adults [see Clinical Studies (14.3)] , the incidence rates of all adjudicated bone fracture were 1.09, 1.59, and 1.79 events per 100 patient-years of follow-up to placebo, canagliflozin 100 mg, and canagliflozin 300 mg, respectively. The fracture imbalance was observed within the first 26 weeks of therapy and remained through the end of the trial. Fractures were more likely to be low trauma (e.g., fall from no more than standing height), and affect the distal portion of upper and lower extremities.

Metformin HCl

The most common adverse reactions (5% or greater incidence) due to initiation of metformin HCl in adults are diarrhea, nausea, vomiting, flatulence, asthenia, indigestion, abdominal discomfort, and headache.

In metformin clinical trials of 29-week duration, a decrease to subnormal levels of previously normal serum vitamin B12levels was observed in approximately 7% of adult patients.

Laboratory and Imaging Tests

Increases in Serum Creatinine and Decreases in eGFR

Initiation of canagliflozin causes an increase in serum creatinine and decrease in estimated GFR. In patients with moderate renal impairment, the increase in serum creatinine generally does not exceed 0.2 mg/dL, occurs within the first 6 weeks of starting therapy, and then stabilizes. Increases that do not fit this pattern should prompt further evaluation to exclude the possibility of acute kidney injury [see Clinical Pharmacology (12.1)] . The acute effect on eGFR reverses after treatment discontinuation suggesting acute hemodynamic changes may play a role in the renal function changes observed with canagliflozin.

Increases in Serum Potassium

In a pooled population of adult patients (N=723) in glycemic control trials with moderate renal impairment (eGFR 45 to less than 60 mL/min/1.73 m^2), increases in serum potassium to greater than 5.4 mEq/L and 15% above occurred in 5.3%, 5.0%, and 8.8% of patients treated with placebo, canagliflozin 100 mg, and canagliflozin 300 mg, respectively. Severe elevations (greater than or equal to 6.5 mEq/L) occurred in 0.4% of patients treated with placebo, no patients treated with canagliflozin 100 mg, and 1.3% of patients treated with canagliflozin 300 mg.

In these patients, increases in potassium were more commonly seen in those with elevated potassium at baseline. Among patients with moderate renal impairment, approximately 84% were taking medications that interfere with potassium excretion, such as potassium-sparing diuretics, angiotensin-converting-enzyme inhibitors, and angiotensin-receptor blockers [see Use in Specific Populations (8.6)].

In CREDENCE, no difference in serum potassium, no increase in adverse events of hyperkalemia, and no increase in absolute (> 6.5 mEq/L) or relative (> upper limit of normal and > 15% increase from baseline) increases in serum potassium were observed in adult patients treated with canagliflozin 100 mg relative to placebo.

Increases in Low-Density Lipoprotein Cholesterol (LDL-C) and non-High-Density Lipoprotein Cholesterol (non-HDL-C)

In the pool of four glycemic control placebo-controlled trials in adults, dose-related increases in LDL-C with canagliflozin were observed. Mean changes (percent changes) from baseline in LDL-C relative to placebo were 4.4 mg/dL (4.5%) and 8.2 mg/dL (8.0%) with canagliflozin 100 mg and canagliflozin 300 mg, respectively. The mean baseline LDL-C levels were 104 to 110 mg/dL across treatment groups.

Dose-related increases in non-HDL-C with canagliflozin were observed in adults. Mean changes (percent changes) from baseline in non-HDL-C relative to placebo were 2.1 mg/dL (1.5%) and 5.1 mg/dL (3.6%) with canagliflozin 100 mg and 300 mg, respectively. The mean baseline non-HDL-C levels were 140 to 147 mg/dL across treatment groups.

Increases in Hemoglobin

In the pool of four placebo-controlled trials in adults of glycemic control, mean changes (percent changes) from baseline in hemoglobin were -0.18 g/dL (-1.1%) with placebo, 0.47 g/dL (3.5%) with canagliflozin 100 mg, and 0.51 g/dL (3.8%) with canagliflozin 300 mg. The mean baseline hemoglobin value was approximately 14.1 g/dL across treatment groups. At the end of treatment, 0.8%, 4.0%, and 2.7% of patients treated with placebo, canagliflozin 100 mg, and canagliflozin 300 mg, respectively, had hemoglobin above the upper limit of normal.

Decreases in Bone Mineral Density

Bone mineral density (BMD) was measured by dual-energy X-ray absorptiometry in a clinical trial of 714 older adults (mean age 64 years) [see Clinical Studies (14.1)] . At 2 years, adult patients randomized to canagliflozin 100 mg and canagliflozin 300 mg had placebo-corrected declines in BMD at the total hip of 0.9% and 1.2%, respectively, and at the lumbar spine of 0.3% and 0.7%, respectively. Additionally, placebo-adjusted BMD declines were 0.1% at the femoral neck for both canagliflozin doses and 0.4% at the distal forearm for patients randomized to canagliflozin 300 mg. The placebo-adjusted change at the distal forearm for patients randomized to canagliflozin 100 mg was 0%.

Clinical Trials in Pediatric Patients Aged 10 Years and Older with Type 2 Diabetes Mellitus

Canagliflozin

Canagliflozin was administered to 84 pediatric patients in a double-blind, placebo-controlled trial of 171 pediatric patients aged 10 to 17 years with a mean exposure to canagliflozin of 48.3 weeks [see Clinical Studies (14.2)] . At baseline, background therapies included metformin monotherapy (46%), metformin and insulin (29%), diet and exercise only (14%), and insulin monotherapy (11%). Approximately 42% were Asian, 42% were White, 11% were Black or African American, 5% were American Indian/Alaska Native, and 36% identified as Hispanic or Latino ethnicity. The mean baseline eGFR was 157.3 mL/min/1.73 m^2, and approximately 16% (24/151) of the trial population with measurements had microalbuminuria or macroalbuminuria. The safety profile of pediatric patients treated with canagliflozin was similar to that observed in adults with type 2 diabetes mellitus.

Metformin HCl

In clinical trials with metformin HCl immediate-release tablets in pediatric patients with type 2 diabetes mellitus, the profile of adverse reactions was similar to that observed in adults.

6.2 Postmarketing Experience

Additional adverse reactions have been identified during post-approval use of canagliflozin and/or metformin. Because these reactions are reported voluntarily from a population of uncertain size, it is generally not possible to reliably estimate their frequency or establish a causal relationship to drug exposure.

Canagliflozin

Metabolism and Nutrition

Ketoacidosis

Renal and Urinary

Acute Kidney Injury

Immune System

Anaphylaxis

Skin and Subcutaneous Tissue

Angioedema

Infections

Urosepsis and Pyelonephritis, Necrotizing Fasciitis of the Perineum (Fournier's gangrene)

Metformin HCl

Hepatobiliary

Cholestatic, hepatocellular, and mixed hepatocellular liver injury

7 DRUG INTERACTIONS

Table 8: Clinically Significant Drug Interactions with INVOKAMET or INVOKAMET XR
Carbonic Anhydrase Inhibitors
Clinical Impact: | Carbonic anhydrase inhibitors frequently cause a decrease in serum bicarbonate and induce non-anion gap, hyperchloremic metabolic acidosis. Concomitant use of these drugs with INVOKAMET or INVOKAMET XR may increase the risk for lactic acidosis.
Intervention: | Consider more frequent monitoring of these patients.
Examples: | Topiramate or other carbonic anhydrase inhibitors (e.g., zonisamide, acetazolamide or dichlorphenamide)
Drugs That Reduce Metformin Clearance
Clinical Impact: | Concomitant use of drugs that interfere with common renal tubular transport systems involved in the renal elimination of metformin (e.g., organic cationic transporter-2 [OCT2] / multidrug and toxin extrusion [MATE] inhibitors could increase systemic exposure to metformin and may increase the risk for lactic acidosis [see Clinical Pharmacology (12.3)].
Intervention: | Consider the benefits and risks of concomitant use.
Examples: | Ranolazine, vandetanib, dolutegravir, and cimetidine
Alcohol
Clinical Impact: | Alcohol is known to potentiate the effect of metformin HCl on lactate metabolism.
Intervention: | Warn patients against excessive alcohol intake while receiving INVOKAMET or INVOKAMET XR.
UGT Enzyme Inducers
Clinical Impact: | UGT enzyme inducers decrease canagliflozin exposure which may reduce the effectiveness of INVOKAMET or INVOKAMET XR.
Intervention: | For patients with eGFR 60 mL/min/1.73 m^2or greater, if an inducer of UGTs is co-administered with INVOKAMET or INVOKAMET XR, increase the total daily dose of canagliflozin to 200 mg in patients currently tolerating INVOKAMET or INVOKAMET XR with a total daily dose of canagliflozin 100 mg. The total daily dose of canagliflozin may be increased to 300 mg in patients currently tolerating canagliflozin 200 mg and who require additional glycemic control. For patients with eGFR less than 60 mL/min/1.73 m^2, if an inducer of UGTs is co-administered with INVOKAMET or INVOKAMET XR, increase the total daily dose of canagliflozin to 200 mg in patients currently tolerating canagliflozin 100 mg [see Dosage and Administration (2.5)and Clinical Pharmacology (12.3)] .
Examples: | Rifampin, phenytoin, phenobarbital, ritonavir
Insulin or Insulin Secretagogues
Clinical Impact: | The risk of hypoglycemia is increased when INVOKAMET or INVOKAMET XR is used concomitantly with insulin secretagogues (e.g., sulfonylurea) or insulin.
Intervention: | Concomitant use may require a lower dosage of the insulin secretagogue or insulin to reduce the risk of hypoglycemia.
Drugs Affecting Glycemic Control
Clinical Impact: | Certain drugs tend to produce hyperglycemia and may lead to loss of glycemic control.
Intervention: | When such drugs are administered to a patient receiving INVOKAMET or INVOKAMET XR, monitor for loss of blood glucose control. When such drugs are withdrawn from a patient receiving INVOKAMET or INVOKAMET XR, monitor for hypoglycemia.
Examples: | Thiazides and other diuretics, corticosteroids, phenothiazines, thyroid products, estrogens, oral contraceptives, phenytoin, nicotinic acid, sympathomimetics, calcium channel blockers, and isoniazid.
Digoxin
Clinical Impact: | Canagliflozin increases digoxin exposure [see Clinical Pharmacology (12.3)] .
Intervention: | Monitor patients taking INVOKAMET or INVOKAMET XR with concomitant digoxin for a need to adjust the dosage of digoxin.
Lithium
Clinical Impact: | Concomitant use of an SGLT2 inhibitor with lithium may decrease serum lithium concentrations.
Intervention: | Monitor serum lithium concentration more frequently during INVOKAMET or INVOKAMET XR initiation and dosage changes.
Drug/Laboratory Test Interference
Positive Urine Glucose Test
Clinical Impact: | SGLT2 inhibitors increase urinary glucose excretion which will lead to positive urine glucose tests.
Intervention: | Monitoring glycemic control with urine glucose tests is not recommended in patients taking SGLT2 inhibitors. Use alternative methods to monitor glycemic control.
Interference with 1,5-anhydroglucitol (1,5-AG) Assay
Clinical Impact: | Measurements of 1,5-AG are unreliable in assessing glycemic control in patients taking SGLT2 inhibitors.
Intervention: | Monitoring glycemic control with 1,5-AG assay is not recommended in patients taking SGLT2 inhibitors. Use alternative methods to monitor glycemic control.

8 USE IN SPECIFIC POPULATIONS

8.1 Pregnancy

Risk Summary

Based on juvenile animal data showing adverse renal effects from canagliflozin, INVOKAMET or INVOKAMET XR is not recommended during the second and third trimesters of pregnancy.

Limited data with INVOKAMET, INVOKAMET XR or canagliflozin in pregnant women are not sufficient to determine a drug-associated risk for major birth defects or miscarriage. Published studies with metformin HCl use during pregnancy have not reported a clear association with metformin HCl and major birth defect or miscarriage risk [see Data]. There are risks to the mother and fetus associated with poorly controlled diabetes in pregnancy [see Clinical Considerations].

In juvenile animal studies, adverse renal pelvic and tubule dilatations that were not reversible were observed in rats when canagliflozin was administered during a period of renal development corresponding to the late second and third trimesters of human pregnancy, at an exposure 0.5-times the 300 mg clinical dose, based on AUC. No adverse developmental effects were observed when metformin HCl was administered to pregnant Sprague Dawley rats and rabbits during the period of organogenesis at doses up to 2- and 6-times, respectively, a 2,000 mg clinical dose, based on body surface area [see Data] .

The estimated background risk of major birth defects is 6–10% in women with pre-gestational diabetes with a HbA1C>7 and has been reported to be as high as 20–25% in women with a HbA1C>10. The estimated background risk of miscarriage for the indicated population is unknown. In the U.S. general population, the estimated background risk of major birth defects and miscarriage in clinically recognized pregnancies is 2–4% and 15–20%, respectively.

Clinical Considerations

Disease-Associated Maternal and/or Embryo/Fetal Risk

Poorly controlled diabetes in pregnancy increases the maternal risk for diabetic ketoacidosis, pre-eclampsia, spontaneous abortions, preterm delivery, and delivery complications. Poorly controlled diabetes increases the fetal risk for major birth defects, stillbirth, and macrosomia related morbidity.

Data

Human Data

Published data from post-marketing studies have not reported a clear association with metformin HCl and major birth defects, miscarriage, or adverse maternal or fetal outcomes when metformin HCl was used during pregnancy. However, these studies cannot definitely establish the absence of any metformin-associated risk because of methodological limitations, including small sample size and inconsistent comparator groups.

Animal Data

Canagliflozin

Canagliflozin dosed directly to juvenile rats from postnatal day (PND) 21 until PND 90 at doses of 4, 20, 65, or 100 mg/kg increased kidney weights and dose dependently increased the incidence and severity of renal pelvic and tubular dilatation at all doses tested. Exposure at the lowest dose was greater than or equal to 0.5-times the 300 mg clinical dose, based on AUC. These outcomes occurred with drug exposure during periods of renal development in rats that correspond to the late second and third trimester of human renal development. The renal pelvic dilatations observed in juvenile animals did not fully reverse within a 1-month recovery period.

In embryo-fetal development studies in rats and rabbits, canagliflozin was administered for intervals coinciding with the first trimester period of organogenesis in humans. No developmental toxicities independent of maternal toxicity were observed when canagliflozin was administered at doses up to 100 mg/kg in pregnant rats and 160 mg/kg in pregnant rabbits during embryonic organogenesis or during a study in which maternal rats were dosed from gestation day (GD) 6 through PND 21, yielding exposures up to approximately 19-times the 300 mg clinical dose, based on AUC.

Metformin HCl

Metformin HCl did not cause adverse developmental effects when administered to pregnant Sprague Dawley rats and rabbits up to 600 mg/kg/day during the period of organogenesis. This represents an exposure of about 2- and 6-times a 2,000 mg clinical dose based on body surface area (mg/m^2) for rats and rabbits, respectively.

Canagliflozin and Metformin HCl

No adverse developmental effects were observed when canagliflozin and metformin HCl were co-administered to pregnant rats during the period of organogenesis at exposures up to 11 and 13 times, respectively, the 300 mg and 2,000 mg clinical doses of canagliflozin and metformin HCl based on AUC.

8.2 Lactation

Risk Summary

There is no information regarding the presence of INVOKAMET, INVOKAMET XR or canagliflozin in human milk, the effects on the breastfed infant, or the effects on milk production. Limited published studies report that metformin is present in human milk [see Data] . However, there is insufficient information on the effects of metformin HCl on the breastfed infant and no available information on the effects of metformin HCl on milk production. Canagliflozin is present in the milk of lactating rats [see Data] . Since human kidney maturation occurs in uteroand during the first 2 years of life when lactational exposure may occur, there may be risk to the developing human kidney.

Because of the potential for serious adverse reactions in a breastfed infant, advise women that use of INVOKAMET or INVOKAMET XR is not recommended while breastfeeding.

Data

Published clinical lactation studies report that metformin is present in human milk which resulted in infant doses approximately 0.11% to 1% of the maternal weight-adjusted dosage and a milk/plasma ratio ranging between 0.13 and 1. However, the studies were not designed to definitely establish the risk of use of metformin HCl during lactation because of small sample size and limited adverse event data collected in infants.

Radiolabeled canagliflozin administered to lactating rats on day 13 post-partum was present at a milk/plasma ratio of 1.40, indicating that canagliflozin and its metabolites are transferred into milk at a concentration comparable to that in plasma. Juvenile rats directly exposed to canagliflozin showed a risk to the developing kidney (renal pelvic and tubular dilatations) during maturation.

8.3 Females and Males of Reproductive Potential

Discuss the potential for unintended pregnancy with premenopausal women as therapy with metformin HCl may result in ovulation in some anovulatory women.

8.4 Pediatric Use

The safety and effectiveness of INVOKAMET and INVOKAMET XR as an adjunct to diet and exercise to improve glycemic control in type 2 diabetes mellitus have been established in pediatric patients aged 10 years and older.

Use of INVOKAMET and INVOKAMET XR for this indication is supported by evidence from a 52-week double-blind, placebo-controlled trial of canagliflozin in 171 pediatric patients aged 10 to 17 years with type 2 diabetes mellitus and in a pediatric pharmacokinetic study [see Clinical Pharmacology (12.3)and Clinical Studies (14.2)] . The safety profile of pediatric patients treated with canagliflozin was similar to that observed in adults with type 2 diabetes mellitus.

The use of INVOKAMET and INVOKAMET XR for this indication is also supported by evidence from adequate and well-controlled trials of metformin HCl immediate-release tablets in adults with additional data from a controlled clinical trial using metformin HCl immediate-release tablets in pediatric patients 10 to 16 years old with type 2 diabetes mellitus, and pharmacokinetic data with metformin HCl extended-release tablets in adults [see Clinical Pharmacology (12.3)and Clinical Studies (14.1, 14.2)]. In the clinical trial with pediatric patients receiving metformin HCl immediate-release tablets, adverse reactions with metformin HCl immediate-release tablets were similar to those described in adults [see Adverse Reactions (6.1)].

The safety and effectiveness of INVOKAMET or INVOKAMET XR for glycemic control in patients with type 2 diabetes mellitus have not been established in pediatric patients under 10 years of age.

The safety and effectiveness of INVOKAMET or INVOKAMET XR have not been established in pediatric patients to reduce the risk of:

- major adverse cardiovascular events (cardiovascular death, nonfatal myocardial infarction and nonfatal stroke) in patients with type 2 diabetes mellitus and established cardiovascular disease (CVD).
- end-stage kidney disease (ESKD), doubling of serum creatinine, cardiovascular (CV) death, and hospitalization for heart failure in patients with type 2 diabetes mellitus and diabetic nephropathy with albuminuria greater than 300 mg/day.

8.5 Geriatric Use

INVOKAMET and INVOKAMET XR

Because renal function abnormalities can occur after initiating canagliflozin, metformin is substantially excreted by the kidney, and aging can be associated with reduced renal function, monitor renal function more frequently after initiating INVOKAMET or INVOKAMET XR in the elderly and then adjust dose based on renal function [see Dosage and Administration (2.4)and Warnings and Precautions (5.1, 5.4)] .

Canagliflozin

In 13 clinical trials of canagliflozin, 2,294 patients 65 years and older, and 351 patients 75 years and older were exposed to canagliflozin. Of these patients, 1,534 patients 65 years and older and 196 patients 75 years and older were exposed to the combination of canagliflozin and metformin HCl [see Clinical Studies (14.1)] . Patients 65 years and older had a higher incidence of adverse reactions related to reduced intravascular volume with canagliflozin (such as hypotension, postural dizziness, orthostatic hypotension, syncope, and dehydration), particularly with the 300 mg daily dose, compared to younger patients; a more prominent increase in the incidence was seen in patients who were 75 years and older [see Dosage and Administration (2.1)and Adverse Reactions (6.1)]. Smaller reductions in HbA1Cwith canagliflozin relative to placebo were seen in older (65 years and older; -0.61% with canagliflozin 100 mg and -0.74% with canagliflozin 300 mg relative to placebo) compared to younger patients (-0.72% with canagliflozin 100 mg and -0.87% with canagliflozin 300 mg relative to placebo).

Metformin HCl

Controlled clinical trials of metformin HCl did not include sufficient numbers of elderly patients to determine whether they respond differently from younger patients, although other reported clinical experience has not identified differences in responses between the elderly and younger patients. The initial and maintenance dosing of metformin HCl should be conservative in patients with advanced age due to the potential for decreased renal function in this population. Any dose adjustment should be based on a careful assessment of renal function [see Contraindications (4), Warnings and Precautions (5.4), and Clinical Pharmacology (12.3)] .

8.6 Renal Impairment

Canagliflozin

The efficacy and safety of canagliflozin for glycemic control were evaluated in a trial that included adult patients with moderate renal impairment (eGFR 30 to less than 50 mL/min/1.73 m^2). These patients had less overall glycemic efficacy, and patients treated with canagliflozin 300 mg per day had increases in serum potassium, which were transient and similar by the end of the trial. Patients with renal impairment using canagliflozin for glycemic control may also be more likely to experience hypotension and may be at higher risk for acute kidney injury [see Warnings and Precautions (5.4)] .

Efficacy and safety trials with canagliflozin did not enroll adult patients with ESKD on dialysis or patients with an eGFR less than 30 mL/min/1.73 m^2 [see Clinical Pharmacology (12.3)] .

Metformin HCl

Metformin is substantially excreted by the kidney, and the risk of metformin accumulation and lactic acidosis increases with the degree of renal impairment. INVOKAMET or INVOKAMET XR is contraindicated in severe renal impairment (eGFR less than 30 mL/min/1.73 m^2) or in patients on dialysis [see Dosage and Administration (2.4), Contraindications (4), Warnings and Precautions (5.1), and Clinical Pharmacology (12.3)].

8.7 Hepatic Impairment

Use of metformin HCl in patients with hepatic impairment has been associated with some cases of lactic acidosis. INVOKAMET or INVOKAMET XR is not recommended in patients with hepatic impairment [see Warnings and Precautions (5.1)].

10 OVERDOSAGE

Overdose of metformin HCl has occurred, including ingestion of amounts greater than 50 grams. Hypoglycemia was reported in approximately 10% of cases, but no causal association with metformin HCl use has been established. Lactic acidosis has been reported in approximately 32% of metformin HCl overdose cases [see Warnings and Precautions (5.1)] .

In the event of an overdose with INVOKAMET or INVOKAMET XR, contact the Poison Help line (1-800-222-1222) or a medical toxicologist for additional overdosage management recommendations. Employ the usual supportive measures (e.g., remove unabsorbed material from the gastrointestinal tract, employ clinical monitoring, and institute supportive treatment) as dictated by the patient's clinical status. Canagliflozin was negligibly removed during a 4-hour hemodialysis session. Canagliflozin is not expected to be dialyzable by peritoneal dialysis. Metformin is dialyzable with a clearance of up to 170 mL/min under good hemodynamic conditions. Therefore, hemodialysis may be useful partly for removal of accumulated metformin from patients in whom INVOKAMET or INVOKAMET XR overdosage is suspected.

11 DESCRIPTION

INVOKAMET ®(canagliflozin and metformin HCl immediate-release tablets) and INVOKAMET ®XR (canagliflozin and metformin HCl extended-release tablets) contain canagliflozin and metformin HCl.

Canagliflozin

Canagliflozin is an inhibitor of SGLT2, the transporter responsible for reabsorbing the majority of glucose filtered by the kidney. Canagliflozin is chemically known as (1 S)-1,5-anhydro-1-[3-[[5-(4-fluorophenyl)-2-thienyl]methyl]-4-methylphenyl]-D-glucitol hemihydrate and its molecular formula and weight are C24H25FO5S•1/2 H2O and 453.53, respectively. The structural formula for canagliflozin is:

Canagliflozin is practically insoluble in aqueous media from pH 1.1 to 12.9.

Metformin HCl

Metformin HCl is a biguanide chemically known as 1,1-Dimethylbiguanide HCl and its molecular formula and weight are C4H11N5● HCl and 165.62, respectively. The structural formula for metformin HCl is:

INVOKAMET and INVOKAMET XR

INVOKAMET or INVOKAMET XR are supplied as film-coated tablets for oral administration. Each 50 mg/500 mg tablet and 50 mg/1,000 mg tablet contains 51 mg of canagliflozin equivalent to 50 mg canagliflozin (anhydrous) and 500 mg or 1,000 mg metformin HCl (equivalent to metformin 389.93 mg and 779.86 mg, respectively).

Each 150 mg/500 mg tablet and 150 mg/1,000 mg tablet contains 153 mg of canagliflozin equivalent to 150 mg canagliflozin (anhydrous) and 500 mg or 1,000 mg metformin HCl (equivalent to metformin 389.93 mg and 779.86 mg, respectively).

INVOKAMET contains the following inactive ingredients: croscarmellose sodium (E468), hypromellose, magnesium stearate (E572), and microcrystalline cellulose (E460[i]). The magnesium stearate is vegetable-sourced. The tablets are finished with a commercially available film-coating consisting of the following inactive ingredients: macrogol/PEG3350 (E1521), polyvinyl alcohol (E1203) (partially hydrolyzed), talc (E553b), titanium dioxide (E171), iron oxide yellow (E172) (50 mg/1,000 mg and 150 mg/500 mg tablets only), iron oxide red (E172) (50 mg/1,000 mg, 150 mg/500 mg and 150 mg/1,000 mg tablets only), and iron oxide black (E172) (150 mg/1,000 mg tablets only).

INVOKAMET XR contains the following inactive ingredients: croscarmellose sodium (E468), hydroxypropyl cellulose (E463), hypromellose, lactose anhydrous, magnesium stearate (E572) (vegetable-sourced), microcrystalline cellulose (E460[i]), polyethylene oxide, and silicified microcrystalline cellulose (50 mg/500 mg and 50 mg/1,000 mg tablets only). The tablets are finished with a commercially available film-coating consisting of the following inactive ingredients: macrogol/PEG3350 (E1521), polyvinyl alcohol (E1203) (partially hydrolyzed), talc (E553b), titanium dioxide (E171), iron oxide red (E172), iron oxide yellow (E172), and iron oxide black (E172) (50 mg/1,000 mg and 150 mg/1,000 mg tablets only).

INVOKAMET XR tablets provide canagliflozin for immediate-release and metformin HCl for extended-release. Each bilayer tablet is compressed from two separate granulates, one for each active ingredient of the tablet, and finished with a film-coating. The metformin HCl extended-release layer is based on a polymer matrix which controls the drug release by passive diffusion through the swollen matrix in combination with tablet erosion.

12 CLINICAL PHARMACOLOGY

12.1 Mechanism of Action

Canagliflozin

SGLT2, expressed in the proximal renal tubules, is responsible for the majority of the reabsorption of filtered glucose from the tubular lumen. Canagliflozin is an inhibitor of SGLT2. By inhibiting SGLT2, canagliflozin reduces reabsorption of filtered glucose and lowers the renal threshold for glucose (RTG), and thereby increases urinary glucose excretion (UGE).

Canagliflozin increases the delivery of sodium to the distal tubule by blocking SGLT2-dependent glucose and sodium reabsorption. This is believed to increase tubuloglomerular feedback and reduce intraglomerular pressure.

Metformin HCl

Metformin HCl is an antihyperglycemic agent which improves glucose tolerance in patients with type 2 diabetes, lowering both basal and postprandial plasma glucose. Metformin HCl decreases hepatic glucose production, decreases intestinal absorption of glucose, and improves insulin sensitivity by increasing peripheral glucose uptake and utilization. With metformin therapy, insulin secretion remains unchanged while fasting insulin levels and day-long plasma insulin response may decrease.

12.2 Pharmacodynamics

Canagliflozin

Following single and multiple oral doses of canagliflozin in adult patients with type 2 diabetes, dose-dependent decreases in RTGand increases in urinary glucose excretion were observed. From a starting RTGvalue of approximately 240 mg/dL, canagliflozin at 100 mg and 300 mg once daily suppressed RTGthroughout the 24-hour period. Data from single oral doses of canagliflozin in healthy volunteers indicate that, on average, the elevation in urinary glucose excretion approaches baseline by about 3 days for doses up to 300 mg once daily. Maximal suppression of mean RTGover the 24-hour period was seen with the 300 mg daily dose to approximately 70 to 90 mg/dL in patients with type 2 diabetes in Phase 1 trials. The reductions in RTGled to increases in mean UGE of approximately 100 g/day in patients with type 2 diabetes treated with either 100 mg or 300 mg of canagliflozin. The 24-h mean RTGat steady state was similar following once daily and twice daily dosing regimens at the same total daily dose of 100 mg or 300 mg. In patients with type 2 diabetes given 100 to 300 mg once daily over a 16-day dosing period, reductions in RTGand increases in urinary glucose excretion were observed over the dosing period. In this trial, plasma glucose declined in a dose-dependent fashion within the first day of dosing.

Cardiac Electrophysiology

In a randomized, double-blind, placebo-controlled, active-comparator, 4-way crossover trial, 60 healthy adult subjects were administered a single oral dose of canagliflozin 300 mg, canagliflozin 1,200 mg (4 times the maximum recommended dose), moxifloxacin, and placebo. No meaningful changes in QTc interval were observed with either the recommended dose of 300 mg or the 1,200 mg dose.

12.3 Pharmacokinetics

INVOKAMET

Administration of INVOKAMET 150 mg/1,000 mg fixed-dose combination with food resulted in no change in overall exposure of canagliflozin. There was no change in metformin AUC; however, the mean peak plasma concentration of metformin was decreased by 16% when administered with food. A delayed time to peak plasma concentration was observed for both components (a delay of 2 hours for canagliflozin and 1 hour for metformin) under fed conditions. These changes are not likely to be clinically meaningful.

INVOKAMET XR

After administration of INVOKAMET XR tablets with a high-fat breakfast, the peak (Cmax) and total (AUC) exposure of canagliflozin were not altered relative to dosing in the fasted state. However, the AUC of metformin increased by approximately 61% and Cmaxincreased by approximately 13%.

Canagliflozin

The pharmacokinetics of canagliflozin is essentially similar in healthy subjects and patients with type 2 diabetes. Following single-dose oral administration of 100 mg and 300 mg of canagliflozin, peak plasma concentrations (median Tmax) of canagliflozin occurs within 1 to 2 hours post-dose. Plasma Cmaxand AUC of canagliflozin increased in a dose-proportional manner from 50 mg to 300 mg. The apparent terminal half-life (t1/2) was 10.6 hours and 13.1 hours for the 100 mg and 300 mg doses, respectively. Steady-state was reached after 4 to 5 days of once-daily dosing with canagliflozin 100 mg to 300 mg. Canagliflozin does not exhibit time-dependent pharmacokinetics and accumulated in plasma up to 36% following multiple doses of 100 mg and 300 mg. The mean systemic exposure (AUC) at steady state was similar following once daily and twice daily dosing regimens at the same total daily dose of 100 mg or 300 mg.

Absorption

Canagliflozin

The mean absolute oral bioavailability of canagliflozin is approximately 65%.

Metformin HCl

The absolute bioavailability of a metformin HCl 500 mg tablet given under fasting conditions is approximately 50% to 60%. Trials using single oral doses of metformin HCl 500 to 1,500 mg, and 850 to 2,550 mg, indicate that there is a lack of dose proportionality with increasing doses, which is due to decreased absorption rather than an alteration in elimination.

Following a single oral dose of 1,000 mg metformin HCl extended-release tablets (two 500 mg tablets) after a meal, the time to reach maximum plasma metformin concentration (Tmax) is achieved at approximately 7–8 hours. In both single and multiple-dose trials in healthy subjects, once daily 1,000 mg (two 500 mg tablets) dosing results in up to 35% higher Cmax, of metformin relative to the immediate-release given as 500 mg twice daily without any change in overall systemic exposure, as measured by AUC.

Distribution

Canagliflozin

The mean steady-state volume of distribution of canagliflozin following a single intravenous infusion in healthy subjects was 83.5 L, suggesting extensive tissue distribution. Canagliflozin is extensively bound to proteins in plasma (99%), mainly to albumin. Protein binding is independent of canagliflozin plasma concentrations. Plasma protein binding is not meaningfully altered in patients with renal or hepatic impairment.

Metformin HCl

The apparent volume of distribution (V/F) of metformin following single oral doses of metformin HCl 850 mg immediate-release tablets averaged 654 ± 358 L. Metformin is negligibly bound to plasma proteins, in contrast to sulfonylureas, which are more than 90% protein bound. Metformin partitions into erythrocytes, most likely as a function of time.

Metabolism

Canagliflozin

O-glucuronidation is the major metabolic elimination pathway for canagliflozin, which is mainly glucuronidated by UGT1A9 and UGT2B4 to two inactive O-glucuronide metabolites. CYP3A4-mediated (oxidative) metabolism of canagliflozin is minimal (approximately 7%) in humans.

Metformin HCl

Intravenous single-dose trials in normal subjects demonstrate that metformin is excreted unchanged in the urine and does not undergo hepatic metabolism (no metabolites have been identified in humans) or biliary excretion.

Excretion

Canagliflozin

Following administration of a single oral [^14C] canagliflozin dose to healthy subjects, 41.5%, 7.0%, and 3.2% of the administered radioactive dose was recovered in feces as canagliflozin, a hydroxylated metabolite, and an O-glucuronide metabolite, respectively. Enterohepatic circulation of canagliflozin was negligible.

Approximately 33% of the administered radioactive dose was excreted in urine, mainly as O-glucuronide metabolites (30.5%). Less than 1% of the dose was excreted as unchanged canagliflozin in urine. Renal clearance of canagliflozin 100 mg and 300 mg doses ranged from 1.30 to 1.55 mL/min.

Mean systemic clearance of canagliflozin was approximately 192 mL/min in healthy subjects following intravenous administration.

Metformin HCl

Renal clearance is approximately 3.5 times greater than creatinine clearance, which indicates that tubular secretion is the major route of metformin elimination. Following oral administration, approximately 90% of the absorbed drug is eliminated via the renal route within the first 24 hours, with a plasma elimination half-life of approximately 6.2 hours. In blood, the elimination half-life is approximately 17.6 hours, suggesting that the erythrocyte mass may be a compartment of distribution.

Specific Populations

Trials characterizing the pharmacokinetics of canagliflozin and metformin after administration of INVOKAMET or INVOKAMET XR were not conducted in patients with renal and hepatic impairment. Descriptions of the individual components in this patient population are described below.

Pediatric Patients

Canagliflozin

The pharmacokinetics and pharmacodynamics of canagliflozin were investigated in pediatric patients aged 10 years and older with type 2 diabetes mellitus. Oral administration of canagliflozin at 100 mg and 300 mg resulted in exposures and responses consistent with those found in adult patients.

Metformin HCl

After administration of a single oral metformin 500 mg immediate-release tablet with food, geometric mean metformin Cmaxand AUC differed less than 5% between pediatric type 2 diabetic patients (12–16 years of age) and gender-and weight-matched healthy adults (20–45 years of age), all with normal renal function.

Patients with Renal Impairment

Canagliflozin

A single-dose, open-label trial evaluated the pharmacokinetics of canagliflozin 200 mg in adult subjects with varying degrees of renal impairment (classified using the MDRD-eGFR formula) compared to healthy subjects.

Renal impairment did not affect the Cmaxof canagliflozin. Compared to healthy adult subjects (N=3; eGFR greater than or equal to 90 mL/min/1.73 m^2), plasma AUC of canagliflozin was increased by approximately 15%, 29%, and 53% in subjects with mild (N=10), moderate (N=9), and severe (N=10) renal impairment, respectively, (eGFR 60 to less than 90, 30 to less than 60, and 15 to less than 30 mL/min/1.73 m^2, respectively), but was similar for ESKD (N=8) subjects and healthy subjects. Increases in canagliflozin AUC of this magnitude are not considered clinically relevant. The glucose lowering pharmacodynamic response to canagliflozin declines with increasing severity of renal impairment [see Contraindications (4)and Warnings and Precautions (5.4)].

Canagliflozin was negligibly removed by hemodialysis.

Metformin HCl

In patients with decreased renal function, the plasma and blood half-life of metformin is prolonged and the renal clearance is decreased [see Contraindications (4)and Warnings and Precautions (5.1)] .

Following a single dose administration of metformin HCl extended-release tablets 500 mg in patients with mild and moderate renal failure (based on measured creatinine clearance), the oral and renal clearance of metformin were decreased by 33% and 50% and 16% and 53%, respectively [see Warnings and Precautions (5.4)] . Metformin peak and systemic exposure was 27% and 61% greater, respectively in mild renal impaired and 74% and 2.36-fold greater in moderate renal impaired patients as compared to healthy subjects [see Contraindications (4)and Warnings and Precautions (5.1)] .

Patients with Hepatic Impairment

Canagliflozin

Relative to adult subjects with normal hepatic function, the geometric mean ratios for Cmaxand AUC∞of canagliflozin were 107% and 110%, respectively, in subjects with Child-Pugh class A (mild hepatic impairment) and 96% and 111%, respectively, in subjects with Child-Pugh class B (moderate hepatic impairment) following administration of a single 300 mg dose of canagliflozin.

These differences are not considered to be clinically meaningful. There is no clinical experience in adult patients with Child-Pugh class C (severe) hepatic impairment [see Warnings and Precautions (5.1)] .

Metformin HCl

No pharmacokinetic trials of metformin HCl tablets have been conducted in patients with hepatic insufficiency [see Warnings and Precautions (5.1)] .

Pharmacokinetic Effects of Age, Body Mass Index (BMI)/Weight, Gender and Race

Canagliflozin

Based on the population PK analysis with data collected from 1,526 adult subjects, age, body mass index (BMI)/weight, gender, and race do not have a clinically meaningful effect on the pharmacokinetics of canagliflozin [see Use in Specific Populations (8.5)] .

Metformin HCl

Metformin pharmacokinetic parameters did not differ significantly between normal subjects and patients with type 2 diabetes when analyzed according to gender.

No trials of metformin pharmacokinetic parameters according to race have been performed.

Canagliflozin

Age had no clinically meaningful effect on the pharmacokinetics of canagliflozin based on a population pharmacokinetic analysis [see Adverse Reactions (6.1)and Use in Specific Populations (8.5)] .

Metformin HCl

Limited data from controlled pharmacokinetic trials of metformin HCl tablets in healthy elderly subjects suggest that total plasma clearance of metformin is decreased, the half-life is prolonged, and Cmaxis increased, compared with healthy young subjects. From these data, it appears that the change in metformin pharmacokinetics with aging is primarily accounted for by a change in renal function [see Warnings and Precautions (5.1, 5.4)and Use in Specific Populations (8.5)] .

Drug Interaction Studies

INVOKAMET and INVOKAMET XR

Pharmacokinetic drug interaction trials with INVOKAMET or INVOKAMET XR have not been performed; however, such trials have been conducted with the individual components canagliflozin and metformin HCl.

Co-administration of multiple doses of canagliflozin (300 mg) and metformin HCl (2,000 mg) given once daily did not meaningfully alter the pharmacokinetics of either canagliflozin or metformin in healthy subjects.

Canagliflozin

In VitroAssessment of Drug Interactions

Canagliflozin did not induce CYP450 enzyme expression (3A4, 2C9, 2C19, 2B6, and 1A2) in cultured human hepatocytes. Canagliflozin did not inhibit the CYP450 isoenzymes (1A2, 2A6, 2C19, 2D6, or 2E1) and weakly inhibited CYP2B6, CYP2C8, CYP2C9, and CYP3A4 based on in vitrostudies with human hepatic microsomes. Canagliflozin is a weak inhibitor of P-gp.

Canagliflozin is also a substrate of drug transporters P-glycoprotein (P-gp) and MRP2.

In VivoAssessment of Drug Interactions

Table 9: Effect of Co–Administered Drugs on Systemic Exposures of Canagliflozin
Co-Administered Drug | Dose of Co-Administered Drug [Single dose unless otherwise noted] | Dose of Canagliflozin | Geometric Mean Ratio (Ratio With/Without Co-Administered Drug) No Effect = 1.0
Co-Administered Drug | Dose of Co-Administered Drug [Single dose unless otherwise noted] | Dose of Canagliflozin | AUC [AUC inf for drugs given as a single dose and AUC 24h for drugs given as multiple doses] (90% CI) | Cmax (90% CI)
See Drug Interactions (7)for the clinical relevance of the following:
Rifampin | 600 mg QD for 8 days | 300 mg | 0.49 (0.44; 0.54) | 0.72 (0.61; 0.84)
No dose adjustments of canagliflozin required for the following:
Cyclosporine | 400 mg | 300 mg QD for 8 days | 1.23 (1.19; 1.27) | 1.01 (0.91; 1.11)
Ethinyl estradiol and levonorgestrel | 0.03 mg ethinyl estradiol and 0.15 mg levonorgestrel | 200 mg QD for 6 days | 0.91 (0.88; 0.94) | 0.92 (0.84; 0.99)
Hydrochlorothiazide | 25 mg QD for 35 days | 300 mg QD for 7 days | 1.12 (1.08; 1.17) | 1.15 (1.06; 1.25)
Metformin HCl | 2,000 mg | 300 mg QD for 8 days | 1.10 (1.05; 1.15) | 1.05 (0.96; 1.16)
Probenecid | 500 mg BID for 3 days | 300 mg QD for 17 days | 1.21 (1.16; 1.25) | 1.13 (1.00; 1.28)
QD = once daily; BID = twice daily

Table 10: Effect of Canagliflozin on Systemic Exposure of Co-Administered Drugs
Co-Administered Drug | Dose of Co-Administered Drug [Single dose unless otherwise noted] | Dose of Canagliflozin | Geometric Mean Ratio (Ratio With/Without Co-Administered Drug) No Effect = 1.0
Co-Administered Drug | Dose of Co-Administered Drug [Single dose unless otherwise noted] | Dose of Canagliflozin |  | AUC [AUC inf for drugs given as a single dose and AUC 24h for drugs given as multiple doses] (90% CI) | Cmax (90% CI)
See Drug Interactions (7)for the clinical relevance of the following:
Digoxin | 0.5 mg QD first day followed by 0.25 mg QD for 6 days | 300 mg QD for 7 days | Digoxin | 1.20 (1.12; 1.28) | 1.36 (1.21; 1.53)
No dose adjustments of co-administered drug required for the following:
Acetaminophen | 1,000 mg | 300 mg BID for 25 days | Acetaminophen | 1.06 [AUC 0–12h] (0.98; 1.14) | 1.00 (0.92; 1.09)
Ethinyl estradiol and levonorgestrel | 0.03 mg ethinyl estradiol and 0.15 mg levonorgestrel | 200 mg QD for 6 days | ethinyl estradiol | 1.07 (0.99; 1.15) | 1.22 (1.10; 1.35)
Ethinyl estradiol and levonorgestrel | 0.03 mg ethinyl estradiol and 0.15 mg levonorgestrel | 200 mg QD for 6 days | Levonorgestrel | 1.06 (1.00; 1.13) | 1.22 (1.11; 1.35)
Glyburide | 1.25 mg | 200 mg QD for 6 days | Glyburide | 1.02 (0.98; 1.07) | 0.93 (0.85; 1.01)
Glyburide | 1.25 mg | 200 mg QD for 6 days | 3-cis-hydroxy-glyburide | 1.01 (0.96; 1.07) | 0.99 (0.91; 1.08)
Glyburide | 1.25 mg | 200 mg QD for 6 days | 4-trans-hydroxy-glyburide | 1.03 (0.97; 1.09) | 0.96 (0.88; 1.04)
Hydrochlorothiazide | 25 mg QD for 35 days | 300 mg QD for 7 days | Hydrochlorothiazide | 0.99 (0.95; 1.04) | 0.94 (0.87; 1.01)
Metformin HCl | 2,000 mg | 300 mg QD for 8 days | Metformin | 1.20 (1.08; 1.34) | 1.06 (0.93; 1.20)
Simvastatin | 40 mg | 300 mg QD for 7 days | Simvastatin | 1.12 (0.94; 1.33) | 1.09 (0.91; 1.31)
Simvastatin | 40 mg | 300 mg QD for 7 days | simvastatin acid | 1.18 (1.03; 1.35) | 1.26 (1.10; 1.45)
Warfarin | 30 mg | 300 mg QD for 12 days | (R)-warfarin | 1.01 (0.96; 1.06) | 1.03 (0.94; 1.13)
Warfarin | 30 mg | 300 mg QD for 12 days | (S)-warfarin | 1.06 (1.00; 1.12) | 1.01 (0.90; 1.13)
Warfarin | 30 mg | 300 mg QD for 12 days | INR | 1.00 (0.98; 1.03) | 1.05 (0.99; 1.12)
QD = once daily; BID = twice daily; INR = International Normalized Ratio

Metformin HCl

Table 11: Effect of Co–Administered Drugs on Plasma Metformin Systemic Exposures
Co-Administered Drug | Dose of Co-Administered Drug [Single dose unless otherwise noted] | Dose of Metformin HCl | Geometric Mean Ratio (Ratio With/Without Co-Administered Drug) No Effect = 1.00
Co-Administered Drug | Dose of Co-Administered Drug [Single dose unless otherwise noted] | Dose of Metformin HCl | AUC [AUC = AUC 0–∞] | Cmax
No dose adjustments required for the following:
Glyburide | 5 mg | 500 mg [Metformin HCl extended-release tablets 500 mg] | 0.98 [Ratio of arithmetic means] | 0.99
Furosemide | 40 mg | 850 mg | 1.09 | 1.22
Nifedipine | 10 mg | 850 mg | 1.16 | 1.21
Propranolol | 40 mg | 850 mg | 0.90 | 0.94
Ibuprofen | 400 mg | 850 mg | 1.05 | 1.07
Drugs that are eliminated by renal tubular secretion increase the accumulation of metformin [see Warnings and Precautions (5)and Drug Interactions (7)]
Cimetidine | 400 mg | 850 mg | 1.40 | 1.61
Carbonic anhydrase inhibitors may cause metabolic acidosis [see Warnings and Precautions (5)and Drug Interactions (7)]
Topiramate [Healthy volunteer study at steady state with topiramate 100 mg every 12 hours and metformin 500 mg every 12 hours for 7 days. Study conducted to assess pharmacokinetics only] | 100 mg | 500 mg | 1.25 [Steady state AUC 0–12h.] | 1.18

Table 12: Effect of Metformin HCl on Co–Administered Drug Systemic Exposures
Co-Administered Drug | Dose of Co-Administered Drug [Single dose unless otherwise noted] | Dose of Metformin HCl | Geometric Mean Ratio (Ratio With/Without Co-Administered Drug) No Effect = 1.00
Co-Administered Drug | Dose of Co-Administered Drug [Single dose unless otherwise noted] | Dose of Metformin HCl | AUC [AUC = AUC 0–∞] | Cmax
No dose adjustments required for the following:
Glyburide | 5 mg | 500 mg [AUC 0–24 hr reported] | 0.78 [Ratio of arithmetic means, p-value of difference <0.05] | 0.63
Furosemide | 40 mg | 850 mg | 0.87 | 0.69
Nifedipine | 10 mg | 850 mg | 1.10 | 1.08
Propranolol | 40 mg | 850 mg | 1.01 | 0.94
Ibuprofen | 400 mg | 850 mg | 0.97 [Ratio of arithmetic means.] | 1.01
Cimetidine | 400 mg | 850 mg | 0.95 | 1.01

Metformin is negligibly bound to plasma proteins and is, therefore, less likely to interact with highly protein-bound drugs such as salicylates, sulfonamides, chloramphenicol, and probenecid.

13 NONCLINICAL TOXICOLOGY

13.1 Carcinogenesis, Mutagenesis, Impairment of Fertility

INVOKAMET and INVOKAMET XR

No animal studies have been conducted with the combined products in INVOKAMET or INVOKAMET XR to evaluate carcinogenesis, mutagenesis, or impairment of fertility. The following data are based on findings in studies with canagliflozin and metformin HCl individually.

Canagliflozin

Carcinogenesis

Carcinogenicity was evaluated in 2-year studies conducted in CD1 mice and Sprague-Dawley rats. Canagliflozin did not increase the incidence of tumors in mice dosed at 10, 30, or 100 mg/kg (less than or equal to 14 times exposure from a 300 mg clinical dose).

Testicular Leydig cell tumors, considered secondary to increased luteinizing hormone (LH), increased significantly in male rats at all doses tested (10, 30, and 100 mg/kg). In a 12-week clinical trial, LH did not increase in males treated with canagliflozin.

Renal tubular adenoma and carcinoma increased significantly in male and female rats dosed at 100 mg/kg, or approximately 12-times exposure from a 300 mg clinical dose. Also, adrenal pheochromocytoma increased significantly in males and numerically in females dosed at 100 mg/kg. Carbohydrate malabsorption associated with high doses of canagliflozin was considered a necessary proximal event in the emergence of renal and adrenal tumors in rats. Clinical trials have not demonstrated carbohydrate malabsorption in humans at canagliflozin doses of up to 2-times the recommended clinical dose of 300 mg.

Mutagenesis

Canagliflozin was not mutagenic with or without metabolic activation in the Ames assay. Canagliflozin was mutagenic in the in vitromouse lymphoma assay with but not without metabolic activation. Canagliflozin was not mutagenic or clastogenic in an in vivooral micronucleus assay in rats and an in vivooral Comet assay in rats.

Metformin HCl

Carcinogenesis

Long-term carcinogenicity studies have been performed in rats (dosing duration of 104 weeks) and mice (dosing duration of 91 weeks) at doses up to and including 900 mg/kg/day and 1,500 mg/kg/day, respectively. These doses are both approximately 4 times the maximum recommended human daily dose of 2,000 mg based on body surface area comparisons. No evidence of carcinogenicity with metformin HCl was found in either male or female mice. Similarly, there was no tumorigenic potential observed with metformin HCl in male rats. There was, however, an increased incidence of benign stromal uterine polyps in female rats treated with 900 mg/kg/day.

Mutagenesis

There was no evidence of a mutagenic potential of metformin HCl in the following in vitrotests: Ames test (S. typhimurium), gene mutation test (mouse lymphoma cells), or chromosomal aberrations test (human lymphocytes). Results in the in vivomouse micronucleus test were also negative.

Impairment of Fertility

Canagliflozin had no effects on the ability of rats to mate and sire or maintain a litter up to the high dose of 100 mg/kg (approximately 14 times and 18 times the 300 mg clinical dose in males and females, respectively), although there were minor alterations in a number of reproductive parameters (decreased sperm velocity, increased number of abnormal sperm, slightly fewer corpora lutea, fewer implantation sites, and smaller litter sizes) at the highest dosage administered.

Fertility of male or female rats was unaffected by metformin HCl when administered at doses as high as 600 mg/kg/day, which is approximately 3 times the maximum recommended human daily dose based on body surface area comparisons.

14 CLINICAL STUDIES

14.1 Glycemic Control Trials in Adults with Type 2 Diabetes Mellitus

The effectiveness of INVOKAMET and INVOKAMET XR have been established in clinical trials with canagliflozin in combination with metformin HCl alone, metformin HCl and sulfonylurea, metformin HCl and sitagliptin, metformin HCl and a thiazolidinedione (i.e., pioglitazone), and metformin HCl and insulin (with or without other anti-hyperglycemic agents). The efficacy of canagliflozin was compared to a dipeptidyl peptidase-4 (DPP-4) inhibitor (sitagliptin), both as add-on combination therapy with metformin HCl and sulfonylurea, and a sulfonylurea (glimepiride), both as add-on combination therapy with metformin HCl.

Canagliflozin as Initial Combination Therapy with Metformin HCl Extended-Release

A total of 1,186 adult patients with type 2 diabetes inadequately controlled with diet and exercise participated in a 26-week double-blind, active-controlled, parallel-group, 5-arm, multicenter trial to evaluate the efficacy and safety of initial therapy with canagliflozin in combination with metformin HCl extended-release. The median age was 56 years, 48% of patients were male, and the mean baseline eGFR was 87.6 mL/min/1.73 m^2. The median duration of diabetes was 1.6 years, and 72% of patients were treatment naïve. After completing a 2-week single-blind placebo run-in period, patients were randomly assigned for a double-blind treatment period of 26 weeks to 1 of 5 treatment groups (Table 13). The metformin HCl extended-release dose was initiated at 500 mg/day for the first week of treatment and then increased to 1,000 mg/day. Metformin HCl extended-release or matching placebo was up-titrated every 2–3 weeks during the next 8 weeks of treatment to a maximum daily dose of 1,500 to 2,000 mg/day, as tolerated; about 90% of patients reached 2,000 mg/day.

At the end of treatment, canagliflozin 100 mg and canagliflozin 300 mg in combination with metformin HCl extended-release resulted in a statistically significant greater improvement in HbA1Ccompared to their respective canagliflozin doses (100 mg and 300 mg) alone or metformin HCl extended-release alone.

Table 13: Results from 26-Week Active-Controlled Clinical Trial of Canagliflozin Alone or Canagliflozin as Initial Combination Therapy with Metformin HCl Extended-Release in Adults with Type 2 Diabetes Mellitus [Intent-to-treat population]
Efficacy Parameter | Metformin HCl extended-release (N=237) | Canagliflozin 100 mg (N=237) | Canagliflozin 300 mg (N=238) | Canagliflozin 100 mg + Metformin HCl extended-release (N=237) | Canagliflozin 300 mg + Metformin HCl extended-release (N=237)
HbA1C(%)
Baseline (mean) | 8.81 | 8.78 | 8.77 | 8.83 | 8.90
Change from baseline (adjusted mean) [There were 121 patients without week 26 efficacy data. Analyses addressing missing data gave consistent results with the results provided in this table.] | -1.30 | -1.37 | -1.42 | -1.77 | -1.78
Difference from canagliflozin 100 mg (adjusted mean) (95% CI) [Least squares mean adjusted for covariates including baseline value and stratification factor] |  |  |  | -0.40 [Adjusted p=0.001] (-0.59, -0.21)
Difference from canagliflozin 300 mg (adjusted mean) (95% CI) |  |  |  |  | -0.36 (-0.56, -0.17)
Difference from metformin HCl extended-release (adjusted mean) (95% CI) |  |  |  | -0.46 (-0.66, -0.27) | -0.48 (-0.67, -0.28)
Percent of patients achieving HbA1C< 7% | 38 | 34 | 39 | 47 [Adjusted p<0.05] | 51

Canagliflozin as Add-on Combination Therapy with Metformin HCl

A total of 1,284 adult patients with type 2 diabetes inadequately controlled on metformin HCl monotherapy (greater than or equal to 2,000 mg/day or at least 1,500 mg/day if higher dose not tolerated) participated in a 26-week, double-blind, placebo- and active-controlled trial to evaluate the efficacy and safety of canagliflozin in combination with metformin HCl. The mean age was 55 years, 47% of patients were male, and the mean baseline eGFR was 89 mL/min/1.73 m^2. Patients already on the required metformin HCl dose (N=1,009) were randomized after completing a 2-week, single-blind, placebo run-in period. Patients taking less than the required metformin HCl dose or patients on metformin HCl in combination with another antihyperglycemic agent (N=275) were switched to metformin HCl monotherapy (at doses described above) for at least 8 weeks before entering the 2-week, single-blind, placebo run-in. After the placebo run-in period, patients were randomized to canagliflozin 100 mg, canagliflozin 300 mg, sitagliptin 100 mg, or placebo, administered once daily as add-on therapy to metformin HCl.

At the end of treatment, canagliflozin 100 mg and 300 mg once daily resulted in a statistically significant improvement in HbA1C(p<0.001 for both doses) compared to placebo when added to metformin HCl. Canagliflozin 100 mg and 300 mg once daily also resulted in a greater proportion of patients achieving an HbA1Cless than 7%, in significant reduction in fasting plasma glucose (FPG), in improved postprandial glucose (PPG), and in percent body weight reduction compared to placebo when added to metformin HCl (see Table 14). Statistically significant (p<0.001 for both doses) mean changes from baseline in systolic blood pressure relative to placebo were -5.4 mmHg and -6.6 mmHg with canagliflozin 100 mg and 300 mg, respectively.

Table 14: Results from 26-Week Placebo-Controlled Clinical Trial of Canagliflozin in Combination with Metformin HCl in Adults with Type 2 Diabetes Mellitus [Intent-to-treat population using last observation in the trial prior to glycemic rescue therapy]
Efficacy Parameter | Placebo + Metformin HCl (N=183) | Canagliflozin 100 mg + Metformin HCl (N=368) | Canagliflozin 300 mg + Metformin HCl (N=367)
HbA1C(%)
Baseline (mean) | 7.96 | 7.94 | 7.95
Change from baseline (adjusted mean) | -0.17 | -0.79 | -0.94
Difference from placebo (adjusted mean) (95% CI) [Least squares mean adjusted for baseline value and stratification factors] |  | -0.62 [p<0.001] (-0.76, -0.48) | -0.77 (-0.91, -0.64)
Percent of patients achieving HbA1C< 7% | 30 | 46 | 58
Fasting Plasma Glucose (mg/dL)
Baseline (mean) | 164 | 169 | 173
Change from baseline (adjusted mean) | 2 | -27 | -38
Difference from placebo (adjusted mean) (95% CI) |  | -30 (-36, -24) | -40 (-46, -34)
2-hour Postprandial Glucose (mg/dL)
Baseline (mean) | 249 | 258 | 262
Change from baseline (adjusted mean) | -10 | -48 | -57
Difference from placebo (adjusted mean) (95% CI) |  | -38 (-49, -27) | -47 (-58, -36)
Body Weight
Baseline (mean) in kg | 86.7 | 88.7 | 85.4
% change from baseline (adjusted mean) | -1.2 | -3.7 | -4.2
Difference from placebo (adjusted mean) (95% CI) |  | -2.5 (-3.1, -1.9) | -2.9 (-3.5, -2.3)

Canagliflozin Compared to Glimepiride, Both as Add-on Combination Therapy with Metformin HCl

A total of 1,450 adult patients with type 2 diabetes inadequately controlled on metformin HCl monotherapy (greater than or equal to 2,000 mg/day or at least 1,500 mg/day if higher dose not tolerated) participated in a 52-week, double-blind, active-controlled trial to evaluate the efficacy and safety of canagliflozin in combination with metformin HCl.

The mean age was 56 years, 52% of patients were male, and the mean baseline eGFR was 90 mL/min/1.73 m^2. Patients tolerating maximally required metformin HCl dose (N=928) were randomized after completing a 2-week, single-blind, placebo run-in period. Other patients (N=522) were switched to metformin HCl monotherapy (at doses described above) for at least 10 weeks, then completed a 2-week single-blind run-in period. After the 2-week run-in period, patients were randomized to canagliflozin 100 mg, canagliflozin 300 mg, or glimepiride (titration allowed throughout the 52-week trial to 6 or 8 mg), administered once daily as add-on therapy to metformin HCl.

As shown in Table 15 and Figure 1, at the end of treatment, canagliflozin 100 mg provided similar reductions in HbA1Cfrom baseline compared to glimepiride when added to metformin HCl therapy. Canagliflozin 300 mg provided a greater reduction from baseline in HbA1Ccompared to glimepiride, and the relative treatment difference was -0.12% (95% CI: −0.22; −0.02). As shown in Table 15, treatment with canagliflozin 100 mg and 300 mg daily provided greater improvements in percent body weight change, relative to glimepiride.

Table 15: Results from 52–Week Clinical Trial Comparing Canagliflozin to Glimepiride in Combination with Metformin HCl in Adults with Type 2 Diabetes Mellitus [Intent-to-treat population using last observation in the trial prior to glycemic rescue therapy]
Efficacy Parameter | Canagliflozin 100 mg + Metformin HCl (N=483) | Canagliflozin 300 mg + Metformin HCl (N=485) | Glimepiride (titrated) + Metformin HCl (N=482)
HbA1C(%)
Baseline (mean) | 7.78 | 7.79 | 7.83
Change from baseline (adjusted mean) | -0.82 | -0.93 | -0.81
Difference from glimepiride (adjusted mean) (95% CI) [Least squares mean adjusted for baseline value and stratification factors] | -0.01 [Canagliflozin + metformin HCl is considered non-inferior to glimepiride + metformin HCl because the upper limit of this confidence interval is less than the pre-specified non-inferiority margin of < 0.3%.] (-0.11, 0.09) | -0.12 (-0.22, -0.02)
Percent of patients achieving HbA1C< 7% | 54 | 60 | 56
Fasting Plasma Glucose (mg/dL)
Baseline (mean) | 165 | 164 | 166
Change from baseline (adjusted mean) | -24 | -28 | -18
Difference from glimepiride (adjusted mean) (95% CI) | -6 (-10, -2) | -9 (-13, -5)
Body Weight
Baseline (mean) in kg | 86.8 | 86.6 | 86.6
% change from baseline (adjusted mean) | -4.2 | -4.7 | 1.0
Difference from glimepiride (adjusted mean) (95% CI) | -5.2 [p<0.001] (-5.7, -4.7) | -5.7 (-6.2, -5.1)

Figure 1: Mean HbA1CChange in Adults with Type 2 Diabetes Mellitus Treated with Canagliflozin or Glimepiride in Combination with Metformin HCl at Each Time Point (Completers) and at Week 52 Using Last Observation Carried Forward (mITT Population)

Canagliflozin as Add-on Combination Therapy with Metformin HCl and Sitagliptin

A total of 217 adult patients with type 2 diabetes inadequately controlled on the combination of metformin HCl (greater than or equal to 1,500 mg/day) and sitagliptin 100 mg/day (or equivalent fixed-dose combination) participated in a 26-week, double-blind, placebo-controlled trial to evaluate the efficacy and safety of canagliflozin in combination with metformin HCl and sitagliptin. The mean age was 57 years, 58% of patients were male, 73% of patients were White, 15% were Asian, and 12% were Black or African American. The mean baseline eGFR was 90 mL/min/1.73 m^2and the mean baseline BMI was 32 kg/m^2. The mean duration of diabetes was 10 years. Eligible patients entered a 2-week, single-blind, placebo run-in period and were subsequently randomized to canagliflozin 100 mg or placebo, administered once daily as add-on to metformin HCl and sitagliptin. Patients with a baseline eGFR of 70 mL/min/1.73 m^2or greater who were tolerating canagliflozin 100 mg and who required additional glycemic control (fasting finger stick 100 mg/dL or greater at least twice within 2 weeks) were up-titrated to canagliflozin 300 mg. While up-titration occurred as early as Week 4, most (90%) patients randomized to canagliflozin were up-titrated to canagliflozin 300 mg by 6 to 8 weeks.

At the end of 26 weeks, canagliflozin once daily resulted in a statistically significant improvement in HbA1C(p<0.001) compared to placebo when added to metformin HCl and sitagliptin (see Table 16).

Table 16: Results from 26−Week Placebo-Controlled Clinical Trial of Canagliflozin in Combination with Metformin HCl and Sitagliptin in Adults with Type 2 Diabetes Mellitus
Efficacy Parameter | Placebo + Metformin HCl and Sitagliptin (N=108 [To preserve the integrity of randomization, all randomized patients were included in the analysis. The patient who was randomized once to each arm was analyzed on canagliflozin.]) | Canagliflozin + Metformin HCl and Sitagliptin (N=109)
HbA1C(%)
Baseline (mean) | 8.40 | 8.50
Change from baseline (adjusted mean) | -0.03 | -0.83
Difference from placebo (adjusted mean) (95% CI) [Early treatment discontinuation before week 26, occurred in 11.0% and 24.1% of canagliflozin and placebo patients, respectively.] [Estimated using a multiple imputation method modeling a "wash-out" of the treatment effect for patients having missing data who discontinued treatment. Missing data was imputed only at week 26 and analyzed using ANCOVA.] |  | -0.81 [p<0.001] (-1.11; -0.51)
Percent of patients achieving HbA1C< 7% [Patients without week 26 efficacy data were considered as non-responders when estimating the proportion achieving HbA 1C< 7%.] | 9 | 28
Fasting Plasma Glucose (mg/dL) [Estimated using a multiple imputation method modeling a "wash-out" of the treatment effect for patients having missing data who discontinued treatment. A mixed model for repeated measures was used to analyze the imputed data.]
Baseline (mean) | 180 | 185
Change from baseline (adjusted mean) | -3 | -28
Difference from placebo (adjusted mean) (95% CI) |  | -25 (-39; -11)

Canagliflozin as Add-on Combination Therapy with Metformin HCl and Sulfonylurea

A total of 469 adult patients with type 2 diabetes inadequately controlled on the combination of metformin HCl (greater than or equal to 2,000 mg/day or at least 1,500 mg/day if higher dose not tolerated) and sulfonylurea (maximal or near-maximal effective dose) participated in a 26-week, double-blind, placebo-controlled trial to evaluate the efficacy and safety of canagliflozin in combination with metformin HCl and sulfonylurea. The mean age was 57 years, 51% of patients were male, and the mean baseline eGFR was 89 mL/min/1.73 m^2. Patients already on the protocol-specified doses of metformin HCl and sulfonylurea (N=372) entered a 2-week, single-blind, placebo run-in period. Other patients (N=97) were required to be on a stable protocol-specified dose of metformin HCl and sulfonylurea for at least 8 weeks before entering the 2-week run-in period. Following the run-in period, patients were randomized to canagliflozin 100 mg, canagliflozin 300 mg, or placebo administered once daily as add-on to metformin HCl and sulfonylurea.

At the end of treatment, canagliflozin 100 mg and 300 mg once daily resulted in a statistically significant improvement in HbA1C(p<0.001 for both doses) compared to placebo when added to metformin HCl and sulfonylurea. Canagliflozin 100 mg and 300 mg once daily also resulted in a greater proportion of patients achieving an HbA1Cless than 7.0%, in a significant reduction in fasting plasma glucose (FPG), and in percent body weight reduction compared to placebo when added to metformin HCl and sulfonylurea (see Table 17).

Table 17: Results from 26–Week Placebo-Controlled Clinical Trial of Canagliflozin in Combination with Metformin HCl and Sulfonylurea in Adults with Type 2 Diabetes Mellitus [Intent-to-treat population using last observation in the trial prior to glycemic rescue therapy]
Efficacy Parameter | Placebo + Metformin HCl and Sulfonylurea (N=156) | Canagliflozin 100 mg + Metformin HCl and Sulfonylurea (N=157) | Canagliflozin 300 mg + Metformin HCl and Sulfonylurea (N=156)
HbA1C(%)
Baseline (mean) | 8.12 | 8.13 | 8.13
Change from baseline (adjusted mean) | -0.13 | -0.85 | -1.06
Difference from placebo (adjusted mean) (95% CI) [Least squares mean adjusted for baseline value and stratification factors] |  | -0.71 [p<0.001] (-0.90, -0.52) | -0.92 (-1.11, -0.73)
Percent of patients achieving HbA1C< 7% | 18 | 43 | 57
Fasting Plasma Glucose (mg/dL)
Baseline (mean) | 170 | 173 | 168
Change from baseline (adjusted mean) | 4 | -18 | -31
Difference from placebo (adjusted mean) (95% CI) |  | -22 (-31, -13) | -35 (-44, -25)
Body Weight
Baseline (mean) in kg | 90.8 | 93.5 | 93.5
% change from baseline (adjusted mean) | -0.7 | -2.1 | -2.6
Difference from placebo (adjusted mean) (95% CI) |  | -1.4 (-2.1, -0.7) | -2.0 (-2.7, -1.3)

Canagliflozin Compared to Sitagliptin, Both as Add-on Combination Therapy with Metformin HCl and Sulfonylurea

A total of 755 adult patients with type 2 diabetes inadequately controlled on the combination of metformin HCl (greater than or equal to 2,000 mg/day or at least 1,500 mg/day if higher dose not tolerated) and sulfonylurea (near-maximal or maximal effective dose) participated in a 52 week, double-blind, active-controlled trial to compare the efficacy and safety of canagliflozin 300 mg versus sitagliptin 100 mg in combination with metformin HCl and sulfonylurea. The mean age was 57 years, 56% of patients were male, and the mean baseline eGFR was 88 mL/min/1.73 m^2. Patients already on protocol-specified doses of metformin HCl and sulfonylurea (N=716) entered a 2-week single-blind, placebo run-in period. Other patients (N=39) were required to be on a stable protocol-specified dose of metformin HCl and sulfonylurea for at least 8 weeks before entering the 2-week run-in period. Following the run-in period, patients were randomized to canagliflozin 300 mg or sitagliptin 100 mg as add-on to metformin HCl and sulfonylurea.

As shown in Table 18 and Figure 2, at the end of treatment, canagliflozin 300 mg provided greater HbA1Creduction compared to sitagliptin 100 mg when added to metformin HCl and sulfonylurea (p<0.05). Canagliflozin 300 mg resulted in a mean percent change in body weight from baseline of -2.5% compared to +0.3% with sitagliptin 100 mg. A mean change in systolic blood pressure from baseline of -5.06 mmHg was observed with canagliflozin 300 mg compared to +0.85 mmHg with sitagliptin 100 mg.

Table 18: Results from 52−Week Clinical Trial Comparing Canagliflozin to Sitagliptin in Combination with Metformin HCl and Sulfonylurea in Adults with Type 2 Diabetes Mellitus [Intent-to-treat population using last observation in the trial prior to glycemic rescue therapy]
Efficacy Parameter | Canagliflozin 300 mg + Metformin HCl and Sulfonylurea (N=377) | Sitagliptin 100 mg + Metformin HCl and Sulfonylurea (N=378)
HbA1C(%)
Baseline (mean) | 8.12 | 8.13
Change from baseline (adjusted mean) | -1.03 | -0.66
Difference from sitagliptin (adjusted mean) (95% CI) [Least squares mean adjusted for baseline value and stratification factors] | -0.37 [Canagliflozin + metformin HCl + sulfonylurea is considered non-inferior to sitagliptin + metformin HCl + sulfonylurea because the upper limit of this confidence interval is less than the pre-specified non-inferiority margin of < 0.3%.] (-0.50, -0.25)
Percent of patients achieving HbA1C< 7% | 48 | 35
Fasting Plasma Glucose (mg/dL)
Baseline (mean) | 170 | 164
Change from baseline (adjusted mean) | -30 | -6
Difference from sitagliptin (adjusted mean) (95% CI) | -24 (-30, -18)
Body Weight
Baseline (mean) in kg | 87.6 | 89.6
% change from baseline (adjusted mean) | -2.5 | 0.3
Difference from sitagliptin (adjusted mean) (95% CI) | -2.8 [p<0.001] (-3.3, -2.2)

Figure 2: Mean HbA1CChange in Adults with Type 2 Diabetes Mellitus Treated with Canagliflozin or Sitagliptin in Combination with Metformin HCl and Sulfonylurea at Each Time Point (Completers) and at Week 52 Using Last Observation Carried Forward (mITT Population)

Canagliflozin as Add-on Combination Therapy with Metformin HCl and Pioglitazone

A total of 342 adult patients with type 2 diabetes inadequately controlled on the combination of metformin HCl (greater than or equal to 2,000 mg/day or at least 1,500 mg/day if higher dose not tolerated) and pioglitazone (30 or 45 mg/day) participated in a 26-week, double--blind, placebo-controlled trial to evaluate the efficacy and safety of canagliflozin in combination with metformin HCl and pioglitazone. The mean age was 57 years, 63% of patients were male, and the mean baseline eGFR was 86 mL/min/1.73 m^2. Patients already on protocol-specified doses of metformin HCl and pioglitazone (N=163) entered a 2-week, single-blind, placebo run-in period. Other patients (N=181) were required to be on stable protocol-specified doses of metformin HCl and pioglitazone for at least 8 weeks before entering the 2-week run-in period. Following the run-in period, patients were randomized to canagliflozin 100 mg, canagliflozin 300 mg, or placebo, administered once daily as add-on to metformin HCl and pioglitazone.

At the end of treatment, canagliflozin 100 mg and 300 mg once daily resulted in a statistically significant improvement in HbA1C(p<0.001 for both doses) compared to placebo when added to metformin HCl and pioglitazone. Canagliflozin 100 mg and 300 mg once daily also resulted in a greater proportion of patients achieving an HbA1Cless than 7%, in significant reduction in fasting plasma glucose (FPG), and in percent body weight reduction compared to placebo when added to metformin HCl and pioglitazone (see Table 19). Statistically significant (p<0.05 for both doses) mean changes from baseline in systolic blood pressure relative to placebo were -4.1 mmHg and -3.5 mmHg with canagliflozin 100 mg and 300 mg, respectively.

Table 19: Results from 26−Week Placebo-Controlled Clinical Trial of Canagliflozin in Combination with Metformin HCl and Pioglitazone in Adults with Type 2 Diabetes Mellitus [Intent-to-treat population using last observation in the trial prior to glycemic rescue therapy]
Efficacy Parameter | Placebo + Metformin HCl and Pioglitazone (N=115) | Canagliflozin 100 mg + Metformin HCl and Pioglitazone (N=113) | Canagliflozin 300 mg + Metformin HCl and Pioglitazone (N=114)
HbA1C(%)
Baseline (mean) | 8.00 | 7.99 | 7.84
Change from baseline (adjusted mean) | -0.26 | -0.89 | -1.03
Difference from placebo (adjusted mean) (95% CI) [Least squares mean adjusted for baseline value and stratification factors] |  | -0.62 [p<0.001] (-0.81, -0.44) | -0.76 (-0.95, -0.58)
Percent of patients achieving HbA1C< 7% | 33 | 47 | 64
Fasting Plasma Glucose (mg/dL)
Baseline (mean) | 164 | 169 | 164
Change from baseline (adjusted mean) | 3 | -27 | -33
Difference from placebo (adjusted mean) (95% CI) |  | -29 (-37, -22) | -36 (-43, -28)
Body Weight
Baseline (mean) in kg | 94.0 | 94.2 | 94.4
% change from baseline (adjusted mean) | -0.1 | -2.8 | -3.8
Difference from placebo (adjusted mean) (95% CI) |  | -2.7 (-3.6, -1.8) | -3.7 (-4.6, -2.8)

Canagliflozin as Add-on Combination Therapy with Insulin (With or Without Other Anti-Hyperglycemic Agents, Including Metformin HCl)

A total of 1,718 adult patients with type 2 diabetes inadequately controlled on insulin greater than or equal to 30 units/day or insulin in combination with other antihyperglycemic agents participated in an 18-week, double-blind, placebo-controlled subtrial of a cardiovascular trial to evaluate the efficacy and safety of canagliflozin in combination with insulin. Of these patients, a subgroup of 432 patients with inadequate glycemic control received canagliflozin or placebo plus metformin HCl and ≥ 30 units/day of insulin over 18 weeks.

In this subgroup, the mean age was 61 years, 67% of patients were male, and the mean baseline eGFR was 81 mL/min/1.73 m^2. Patients on metformin HCl in combination with basal, bolus, or basal/bolus insulin for at least 10 weeks entered a 2-week, single-blind, placebo run-in period. Approximately 74% of these patients were on a background of metformin HCl and basal/bolus insulin regimen. After the run-in period, patients were randomized to canagliflozin 100 mg, canagliflozin 300 mg, or placebo, administered once daily as add-on to metformin HCl and insulin. The mean daily insulin dose at baseline was 93 units, which was similar across treatment groups.

At the end of treatment, canagliflozin 100 mg and 300 mg once daily resulted in a statistically significant improvement in HbA1C(p<0.001 for both doses) compared to placebo when added to metformin HCl and insulin. Canagliflozin 100 mg and 300 mg once daily also resulted in a greater proportion of patients achieving an HbA1Cless than 7%, in significant reductions in fasting plasma glucose (FPG), and in percent body weight reductions compared to placebo (see Table 20). Statistically significant (p=0.023 for the 100 mg and p<0.001 for the 300 mg dose) mean change from baseline in systolic blood pressure relative to placebo was –3.5 mmHg and -6 mmHg with canagliflozin 100 mg and 300 mg, respectively. Fewer patients on canagliflozin in combination with metformin HCl and insulin required glycemic rescue therapy: 3.6% of patients receiving canagliflozin 100 mg, 2.7% of patients receiving canagliflozin 300 mg, and 6.2% of patients receiving placebo. An increased incidence of hypoglycemia was observed in this trial, which is consistent with the expected increase of hypoglycemia when an agent not associated with hypoglycemia is added to insulin [see Warnings and Precautions (5.6)and Adverse Reactions (6.1)] .

Table 20: Results from 18–Week Placebo-Controlled Clinical Trial of Canagliflozin in Combination with Metformin HCl and Insulin ≥ 30 Units/Day in Adults with Type 2 Diabetes Mellitus [Intent-to-treat population using last observation in the trial prior to glycemic rescue therapy]
Efficacy Parameter | Placebo + Metformin HCl + Insulin (N=145) | Canagliflozin 100 mg + Metformin HCl + Insulin (N=139) | Canagliflozin 300 mg + Metformin HCl + Insulin (N=148)
HbA1C(%)
Baseline (mean) | 8.15 | 8.20 | 8.22
Change from baseline (adjusted mean) | 0.03 | -0.64 | -0.79
Difference from placebo (adjusted mean) (95% CI) [Least squares mean adjusted for baseline value and stratification factors] |  | -0.66 [p≤0.001] (-0.81, -0.51) | -0.82 (-0.96, -0.67)
Percent of patients achieving HbA1C< 7% | 9 | 19 [p≤0.01] | 29
Fasting Plasma Glucose (mg/dL)
Baseline | 163 | 168 | 167
Change from baseline (adjusted mean) | 1 | -16 | -24
Difference from placebo (adjusted mean) (97.5% CI) |  | -16 (-28, -5) | -25 (-36, -14)
Body Weight
Baseline (mean) in kg | 102.3 | 99.7 | 101.1
% change from baseline (adjusted mean) | 0.0 | -1.7 | -2.7
Difference from placebo (adjusted mean) (97.5% CI) |  | -1.7 (-2.4, -1.0) | -2.7 (-3.4, -2.0)

14.2 Glycemic Control Trial in Pediatric Patients Aged 10 Years and Older with Type 2 Diabetes Mellitus

Glycemic Control Trial of Canagliflozin in Pediatric Patients Aged 10 years and Older with Type 2 Diabetes Mellitus

In a double-blind, placebo-controlled, parallel-group pediatric trial (NCT03170518), 171 pediatric patients aged 10 to 17 years with inadequately controlled type 2 diabetes mellitus (HbA1C≥6.5% and ≤11.0%) were randomized to canagliflozin (84 patients) or placebo (87 patients) as add-on to diet and exercise, metformin HCl (≥1,000 mg per day or maximally tolerated dosage), insulin, or a combination of metformin HCl and insulin, for a total of 52-weeks. At Week 13, patients in the canagliflozin arm whose HbA1Cwas ≥7.0% and eGFR ≥60 mL/min/1.73m^2were re-randomized to either continue on canagliflozin 100 mg orally once daily (n=16) or to up-titrate to 300 mg orally once daily (n=17).

At baseline, background therapies included diet and exercise only (14%), insulin monotherapy (11%), metformin HCl and insulin (29%), and metformin HCl monotherapy (46%). The mean HbA1Cat baseline was 8.0% and the mean duration of type 2 diabetes mellitus was 2 years. The mean eGFR at baseline was 157.3 mL/min/1.73 m^2, and approximately 16% (24/151) of the trial population with measurements had microalbuminuria or macroalbuminuria. Patients with an eGFR less than 60 mL/min/1.73 m^2were not enrolled in the trial; no patients in the trial reached an eGFR < 60 mL/min/1.72m^2. The mean age was 14.3 years, 47% were under 15 years of age, and 68% were female. Approximately 42% were Asian, 42% were White, 11% were Black or African American, 5% were American Indian/Alaska Native, and 36% were of Hispanic or Latino ethnicity. The mean BMI was 30.8 kg/m^2(range 18–57 kg/m^2) and the mean BMI Z-score was 1.84.

At Week 26, treatment with canagliflozin provided statistically significant improvement in HbA1Cfrom baseline, compared with placebo (see Table 21).

The treatment effect with canagliflozin was consistent in the subgroup of patients with metformin with or without insulin as background therapy [adjusted mean change in HbA1Crelative to placebo from baseline to Week 26 was –0.74% (95% CI -1.37, -0.11; p = 0.02)].

Table 21: Results at Week 26 in a Placebo-Controlled Trial of Canagliflozin in Combination with Metformin HCl and/or Insulin or as Monotherapy in Pediatric Patients Aged 10 Years and Older with Type 2 Diabetes Mellitus [Modified intent-to-treat set (All randomized and treated patients with baseline HbA 1C measurement).]
Efficacy Parameter | Placebo (N=87) | Canagliflozin (N=84)
HbA1C(%)
Baseline (mean) | 8.3 | 7.8
Change from baseline [Multiple imputation using retrieved dropout approach with 1,000 iterations for missing data (canagliflozin N=7 (8.3%), placebo N=7 (8.1%) for HbA 1C and canagliflozin N=9 (10.7%), placebo N=7 (8.1%) for FPG).] [Least-Square Mean from Analysis of Covariance (ANCOVA) adjusted for baseline value, baseline age stratum (< 15 years vs 15 to < 18 years) and baseline antihyperglycemic agent (AHA) background (i.e., diet and exercise only, metformin monotherapy, insulin monotherapy, or combination of insulin and metformin).] | 0.34 | -0.38
Difference from placebo 95% CI |  | -0.73 (-1.26, -0.19) [P-value=0.008 (two-sided)]
FPG (mg/dL)
Baseline (mean) | 156.5 | 154.8
Change from baseline | 17.29 | -8.22
Difference from placebo 95% CI |  | -25.51 (-49.55, -1.47) [Not evaluated for statistical significance, not part of sequential testing procedure.]

Glycemic Control Trial of Metformin HCl Immediate-Release in Pediatric Patients Aged 10 to 16 Years with Type 2 Diabetes Mellitus

A double-blind, placebo-controlled trial was conducted in pediatric patients aged 10 to 16 years with type 2 diabetes mellitus (mean FPG 182.2 mg/dL), where patients were treated with metformin HCl immediate-release tablets (up to 2,000 mg/day) for up to 16 weeks (mean duration of treatment 11 weeks). The results are displayed in Table 22.

Table 22: Mean Change in Fasting Plasma Glucose at Week 16 Comparing Metformin HCl versus Placebo in Pediatric Patients [Pediatric patients mean age 13.8 years (range 10–16 years)] with Type 2 Diabetes Mellitus
 | Metformin HCl | Placebo | p-value
FPG Baseline Change at Final Visit | (n=37) 162.4 -42.9 | (n=36) 192.3 21.4 | <0.001

Mean baseline body weight was 205 lbs and 189 lbs in the metformin HCl immediate-release and placebo arms, respectively. Mean change in body weight from baseline to week 16 was -3.3 lbs and -2.0 lbs in the metformin HCl and placebo arms, respectively.

14.3 Canagliflozin Cardiovascular Outcomes in Adults with Type 2 Diabetes Mellitus and Atherosclerotic Cardiovascular Disease

Canagliflozin is indicated to reduce the risk of major adverse cardiovascular events in adults with type 2 diabetes mellitus and established cardiovascular disease (CVD).

The CANVAS and CANVAS-R trials were multicenter, multi-national, randomized, double-blind parallel group, with similar inclusion and exclusion criteria. Patients eligible for enrollment in both CANVAS and CANVAS-R trials were: 30 years of age or older and had established, stable, cardiovascular, cerebrovascular, peripheral artery disease (66% of the enrolled population) or were 50 years of age or older and had two or more other specified risk factors for cardiovascular disease (34% of the enrolled population).

The integrated analysis of the CANVAS and CANVAS-R trials compared the risk of Major Adverse Cardiovascular Event (MACE) between canagliflozin and placebo when these were added to and used concomitantly with standard of care treatments for diabetes and atherosclerotic cardiovascular disease. The primary endpoint, MACE, was the time to first occurrence of a three-part composite outcome which included cardiovascular death, non-fatal myocardial infarction and non-fatal stroke.

In CANVAS, patients were randomly assigned 1:1:1 to canagliflozin 100 mg, canagliflozin 300 mg, or matching placebo. In CANVAS-R, patients were randomly assigned 1:1 to canagliflozin 100 mg or matching placebo, and titration to 300 mg was permitted at the investigator's discretion (based on tolerability and glycemic needs) after Week 13. Concomitant antidiabetic and atherosclerotic therapies could be adjusted, at the discretion of investigators, to ensure participants were treated according to the standard care for these diseases.

A total of 10,134 adult patients were treated (4,327 in CANVAS and 5,807 in CANVAS-R; total of 4,344 randomly assigned to placebo and 5,790 to canagliflozin) for a mean exposure duration of 149 weeks (223 weeks [4.3 years] in CANVAS and 94 weeks [1.8 years] in CANVAS-R) .Approximately 78% of the trial population was White, 13% was Asian, and 3% was Black or African American. The mean age was 63 years and approximately 64% were male.

The mean HbA1Cat baseline was 8.2% and mean duration of diabetes was 13.5 years with 70% of patients having had diabetes for 10 years or more. Approximately 31%, 21% and 17% reported a past history of neuropathy, retinopathy and nephropathy, respectively, and the mean eGFR 76 mL/min/1.73 m^2. At baseline, patients were treated with one (19%) or more (80%) antidiabetic medications including metformin HCl (77%), insulin (50%), and sulfonylurea (43%).

At baseline, the mean systolic blood pressure was 137 mmHg, the mean diastolic blood pressure was 78 mmHg, the mean LDL was 89 mg/dL, the mean HDL was 46 mg/dL, and the mean urinary albumin to creatinine ratio (UACR) was 115 mg/g. At baseline, approximately 80% of patients were treated with renin angiotensin system inhibitors, 53% with beta-blockers, 13% with loop diuretics, 36% with non-loop diuretics, 75% with statins, and 74% with antiplatelet agents (mostly aspirin). During the trial, investigators could modify anti-diabetic and cardiovascular therapies to achieve local standard of care treatment targets with respect to blood glucose, lipid, and blood pressure. More patients receiving canagliflozin compared to placebo initiated anti-thrombotics (5.2% vs 4.2%) and statins (5.8% vs 4.8%) during the trial.

For the primary analysis, a stratified Cox proportional hazards model was used to test for non-inferiority against a pre-specified risk margin of 1.3 for the hazard ratio of MACE.

In the integrated analysis of CANVAS and CANVAS-R trials, canagliflozin reduced the risk of first occurrence of MACE. The estimated hazard ratio (95% CI) for time to first MACE was 0.86 (0.75, 0.97). Refer to Table 23. Vital status was obtained for 99.6% of patients across the trials. The Kaplan-Meier curve depicting time to first occurrence of MACE is shown in Figure 3.

Table 23: Treatment Effect for the Primary Composite Endpoint, MACE, and its Components in the Integrated Analysis of CANVAS and CANVAS-R Trials in Adults with Type 2 Diabetes Mellitus and Atherosclerotic Cardiovascular Disease [Intent-To-Treat Analysis Set]
 | Placebo N=4,347 (%) | Canagliflozin N=5,795 (%) | Hazard ratio (95% CI) [Stratified Cox-proportional hazards model with treatment as a factor and stratified by the trial and by prior CV disease]
Composite of cardiovascular death, non-fatal myocardial infarction, non-fatal stroke (time to first occurrence) [P-value for superiority (2-sided) = 0.0158] , [Number and percentage of first events] , [Due to pooling of unequal randomization ratios, Cochran-Mantel-Haenszel weights were applied to calculate percentages] , | 426 (10.4) | 585 (9.2) | 0.86 (0.75, 0.97)
Non-fatal myocardial infarction , | 159 (3.9) | 215 (3.4) | 0.85 (0.69, 1.05)
Non-fatal Stroke , | 116 (2.8) | 158 (2.5) | 0.90 (0.71, 1.15)
Cardiovascular Death , | 185 (4.6) | 268 (4.1) | 0.87 (0.72, 1.06)

Figure 3: Time to First Occurrence of MACE

14.4 Canagliflozin Renal and Cardiovascular Outcomes in Adults with Diabetic Nephropathy and Albuminuria

Canagliflozin is indicated to reduce the risk of end-stage kidney disease (ESKD), doubling of serum creatinine, cardiovascular (CV) death, and hospitalization for heart failure in adults with type 2 diabetes mellitus and diabetic nephropathy with albuminuria ˃ 300 mg/day.

The Canagliflozin and Renal Events in Diabetes with Established Nephropathy Clinical Evaluation Trial (CREDENCE) was a multinational, randomized, double-blind, placebo-controlled trial comparing canagliflozin with placebo in adult patients with type 2 diabetes mellitus, an eGFR ≥ 30 to < 90 mL/min/1.73 m^2and albuminuria (urine albumin/creatinine ˃ 300 to ≤ 5,000 mg/g) who were receiving standard of care including a maximum-tolerated, labeled daily dose of an angiotensin-converting enzyme inhibitor (ACEi) or angiotensin receptor blocker (ARB).

The primary objective of CREDENCE was to assess the efficacy of canagliflozin relative to placebo in reducing the composite endpoint of end stage kidney disease (ESKD), doubling of serum creatinine, and renal or CV death.

Patients were randomized to receive canagliflozin 100 mg (N=2,202) or placebo (N=2,199) and treatment was continued until the initiation of dialysis or renal transplantation.

The median follow-up duration for the 4,401 randomized subjects was 137 weeks. Vital status was obtained for 99.9% of subjects.

The population was 67% White, 20% Asian, and 5% Black or African American; 32% were of Hispanic or Latino ethnicity. The mean age was 63 years and 66% were male.

At randomization, the mean HbA1Cwas 8.3%, the median urine albumin/creatinine was 927 mg/g, the mean eGFR was 56.2 mL/min/1.73 m^2, 50% had prior CV disease, and 15% reported a history of heart failure. The most frequent antihyperglycemic agents (AHA) medications used at baseline were insulin (66%), biguanides (58%), and sulfonylureas (29%). Nearly all subjects (99.9%) were on ACEi or ARB at randomization, approximately 60% were taking an anti-thrombotic agent (including aspirin), and 69% were on a statin.

The primary composite endpoint in the CREDENCE trial was the time to first occurrence of ESKD (defined as an eGFR < 15 mL/min/1.73 m^2, initiation of chronic dialysis or renal transplant), doubling of serum creatinine, and renal or CV death. Canagliflozin 100 mg significantly reduced the risk of the primary composite endpoint based on a time-to-event analysis [HR: 0.70; 95% CI: 0.59, 0.82; p<0.0001] (see Figure 4). The treatment effect reflected a reduction in progression to ESKD, doubling of serum creatinine and cardiovascular death as shown in Table 24 and Figure 4. There were few renal deaths during the trial. Canagliflozin 100 mg also significantly reduced the risk of hospitalization for heart failure [HR: 0.61; 95% CI: 0.47 to 0.80; p<0.001].

Table 24: Analysis of Primary Endpoint (including the Individual Components) and Secondary Endpoints from the CREDENCE Trial in Adults with Diabetic Nephropathy and Albuminuria
 | Placebo |  | canagliflozin
Endpoint | N=2,199 (%) | Event Rate [Event rate per 100 patient-years.] | N=2,202 (%) | Event Rate | HR [Hazard ratio (canagliflozin compared to placebo), 95% CI and p-value are estimated using a stratified Cox proportional hazards model including treatment as the explanatory variable and stratified by screening eGFR (≥ 30 to < 45, ≥ 45 to < 60, ≥ 60 to < 90 mL/min/1.73 m 2). HR is not presented for renal death due to the small number of events in each group.] (95% CI)
Primary Composite Endpoint (ESKD, doubling of serum creatinine, renal death, or CV death) | 340 (15.5) | 6.1 | 245 (11.1) | 4.3 | 0.70 (0.59, 0.82) [P-value <0.0001]
ESKD | 165 (7.5) | 2.9 | 116 (5.3) | 2.0 | 0.68 (0.54, 0.86)
Doubling of serum creatinine | 188 (8.5) | 3.4 | 118 (5.4) | 2.1 | 0.60 (0.48, 0.76)
Renal death | 5 (0.2) | 0.1 | 2 (0.1) | 0.0
CV death | 140 (6.4) | 2.4 | 110 (5.0) | 1.9 | 0.78 (0.61, 1.00)
CV death or hospitalization for heart failure | 253 (11.5) | 4.5 | 179 (8.1) | 3.1 | 0.69 (0.57, 0.83) [P-value <0.001]
CV death, non-fatal myocardial infarction or non-fatal stroke | 269 (12.2) | 4.9 | 217 (9.9) | 3.9 | 0.80 (0.67, 0.95) [P-value <0.02]
Non-fatal myocardial infarction | 87 (4.0) | 1.6 | 71 (3.2) | 1.3 | 0.81 (0.59, 1.10)
Non-fatal stroke | 66 (3.0) | 1.2 | 53 (2.4) | 0.9 | 0.80 (0.56, 1.15)
Hospitalization for heart failure | 141 (6.4) | 2.5 | 89 (4.0) | 1.6 | 0.61 (0.47, 0.80)
ESKD, doubling of serum creatinine or renal death | 224 (10.2) | 4.0 | 153 (6.9) | 2.7 | 0.66 (0.53, 0.81)
Intent-To-Treat Analysis Set (time to first occurrence)
The individual components do not represent a breakdown of the composite outcomes, but rather the total number of subjects experiencing an event during the course of the trial.

The Kaplan-Meier curve (Figure 4) shows time to first occurrence of the primary composite endpoint of ESKD, doubling of serum creatinine, renal death, or CV death. The curves begin to separate by Week 52 and continue to diverge thereafter.

Figure 4: CREDENCE: Time to First Occurrence of the Primary Composite Endpoint

16 HOW SUPPLIED/STORAGE AND HANDLING

INVOKAMET ®tablets are available in bottles of 60 in the strengths listed below:

INVOKAMET | TABLET STRENGTH
canagliflozin/metformin HCl tablets | 50 mg/500 mg | 50 mg/1,000 mg | 150 mg/500 mg | 150 mg/1,000 mg
Color | White | Beige | Yellow | Purple
Tablet Identification | CM | CM | CM | CM
Tablet Identification | 155 | 551 | 215 | 611
Tablet Identification | Capsule-shaped, film-coated tablets
NDC | 50458-540-60 | 50458-541-60 | 50458-542-60 | 50458-543-60

INVOKAMET ®XR tablets are available in bottles of 60 in the strengths listed below:

INVOKAMET XR | TABLET STRENGTH
canagliflozin/metformin HCl extended-release tablets | 50 mg/500 mg | 50 mg/1,000 mg | 150 mg/500 mg | 150 mg/1,000 mg
Color | Almost White to Light Orange | Pink | Orange | Reddish Brown
Tablet Identification | CM1 | CM3 | CM2 | CM4
Tablet Identification | Oblong, biconvex, film-coated tablets, a thin line on the tablet side may be visible.
NDC | 50458-940-01 | 50458-941-01 | 50458-942-01 | 50458-943-01

Storage and Handling

Keep out of reach of children.

Store at 20 °C to 25 °C (68 °F to 77 °F); excursions permitted between 15 °C to 30°C (59 °F to 86 °F) [see USP Controlled Room Temperature]. Store and dispense in the original container. Storage in a pill box or pill organizer is allowed for up to 30 days.

17 PATIENT COUNSELING INFORMATION

Advise the patient to read the FDA-Approved Patient Labeling (Medication Guide) .

Lactic Acidosis

Explain the risks of lactic acidosis, its symptoms, and conditions that predispose to its development, as noted in Warnings and Precautions (5.1). Advise patients to discontinue INVOKAMET or INVOKAMET XR immediately and to promptly notify their health care provider if unexplained hyperventilation, myalgias, malaise, unusual somnolence or other nonspecific symptoms occur. Once a patient is stabilized on INVOKAMET or INVOKAMET XR, gastrointestinal symptoms, which are common during initiation of metformin HCl, are unlikely to recur. Later occurrence of gastrointestinal symptoms could be due to lactic acidosis or other serious disease.

Counsel patients against excessive alcohol intake while receiving INVOKAMET or INVOKAMET XR.

Inform patients about importance of regular testing of renal function and hematological parameters while receiving INVOKAMET or INVOKAMET XR.

Instruct patients to inform their doctor that they are taking INVOKAMET or INVOKAMET XR prior to any surgical or radiological procedure, as temporary discontinuation of INVOKAMET or INVOKAMET XR may be required until renal function has been confirmed to be normal [see Warnings and Precautions (5.1)] .

Diabetic Ketoacidosis in Patients with Type 1 Diabetes Mellitus and Other Ketoacidosis

Inform patients that INVOKAMET or INVOKAMET XR can cause potentially fatal ketoacidosis and that type 2 diabetes mellitus and pancreatic disorders (e.g., history of pancreatitis or pancreatic surgery) are risk factors.

Educate all patients on precipitating factors (such as insulin dose reduction or missed doses, infection, reduced caloric intake, ketogenic diet, surgery, dehydration, and alcohol abuse) and symptoms of ketoacidosis (including nausea, vomiting, abdominal pain, tiredness, and labored breathing). Inform patients that blood glucose may be normal even in the presence of ketoacidosis.

Advise patients that they may be asked to monitor ketones. If symptoms of ketoacidosis occur, instruct patients to discontinue INVOKAMET or INVOKAMET XR and seek medical attention immediately [see Warnings and Precautions (5.2)].

Lower Limb Amputation

Inform patients that INVOKAMET or INVOKAMET XR is associated with an increased risk of amputations. Counsel patients about the importance of routine preventative foot care. Instruct patients to monitor for new pain or tenderness, sores or ulcers, or infections involving the leg or foot and to seek medical advice immediately if such signs or symptoms develop [see Warnings and Precautions (5.3)] .

Volume Depletion

Inform patients that symptomatic hypotension may occur with INVOKAMET or INVOKAMET XR and advise them to contact their doctor if they experience such symptoms [see Warnings and Precautions (5.4)] . Inform patients that dehydration may increase the risk for hypotension and to have adequate fluid intake.

Serious Urinary Tract Infections

Inform patients of the potential for urinary tract infections, which may be serious. Provide them with information on the symptoms of urinary tract infections. Advise them to seek medical advice if such symptoms occur [see Warnings and Precautions (5.5)] .

Hypoglycemia with Concomitant Use with Insulin or Insulin Secretagogues

Inform patients that hypoglycemia has been reported when INVOKAMET or INVOKAMET XR is used with insulin or insulin secretagogues. Educate patients or caregivers on the signs and symptoms of hypoglycemia [see Warnings and Precautions (5.6)].

Necrotizing Fasciitis of the Perineum (Fournier's Gangrene)

Inform patients that necrotizing infections of the perineum (Fournier's gangrene) have occurred with INVOKAMET or INVOKAMET XR. Counsel patients to promptly seek medical attention if they develop pain or tenderness, redness, or swelling of the genitals or the area from the genitals back to the rectum, along with a fever above 100.4°F or malaise [see Warnings and Precautions (5.7)] .

Genital Mycotic Infections in Females (e.g., Vulvovaginitis)

Inform female patients that vaginal yeast infection (e.g., vulvovaginitis) may occur and provide them with information on the signs and symptoms of a vaginal yeast infection. Advise them of treatment options and when to seek medical advice [see Warnings and Precautions (5.8)] .

Genital Mycotic Infections in Males (e.g., Balanitis or Balanoposthitis)

Inform male patients that yeast infection of penis (e.g., balanitis or balanoposthitis) may occur, especially in uncircumcised males and patients with prior history. Provide them with information on the signs and symptoms of balanitis and balanoposthitis (rash or redness of the glans or foreskin of the penis). Advise them of treatment options and when to seek medical advice [see Warnings and Precautions (5.8)] .

Hypersensitivity Reactions

Inform patients that serious hypersensitivity reactions, such as urticaria, rash, anaphylaxis, and angioedema, have been reported with canagliflozin. Advise patients to report immediately any signs or symptoms suggesting allergic reaction and to discontinue drug until they have consulted prescribing physicians [see Warnings and Precautions (5.9)] .

Bone Fracture

Inform patients that bone fractures have been reported in adult patients taking canagliflozin. Provide them with information on factors that may contribute to fracture risk [see Warnings and Precautions (5.10)] .

Vitamin B12Deficiency

Inform patients about importance of regular hematological parameters while receiving INVOKAMET or INVOKAMET XR [see Warnings and Precautions (5.11)].

Laboratory Tests

Inform patients that they will test positive for glucose in their urine while on INVOKAMET or INVOKAMET XR [see Drug Interactions (7)] .

Females of Reproductive Age

Advise pregnant women, and females of reproductive potential of the potential risk to a fetus with treatment with INVOKAMET or INVOKAMET XR [see Use in Specific Populations (8.1)] . Instruct females of reproductive potential to report pregnancies to their physicians as soon as possible.

Inform females that treatment with INVOKAMET or INVOKAMET XR may result in ovulation in some premenopausal anovulatory women which may lead to unintended pregnancy [see Use in Specific Populations (8.3)] .

Lactation

Advise women that breastfeeding is not recommended during treatment with INVOKAMET or INVOKAMET XR [see Use in Specific Populations (8.2)] .

Administration

Instruct patients to keep INVOKAMET or INVOKAMET XR in the original bottle to protect from moisture. Advise patients that storage in a pill box or pill organizer is allowed for up to 30 days.

Instruct patients to take INVOKAMET only as prescribed twice daily with food. If a dose is missed, advise patients not to take two doses of INVOKAMET at the same time.

Instruct patients to take INVOKAMET XR only as prescribed once daily with the morning meal. If a dose is missed, advise patients to take it as soon as it is remembered unless it is almost time for the next dose, in which case patients should skip the missed dose and take the medicine at the next regularly scheduled time. Advise patients not to take more than two tablets of INVOKAMET XR at the same time.

Instruct patients that INVOKAMET XR must be swallowed whole and never crushed, cut, or chewed, and that the inactive ingredients may occasionally be eliminated in the feces as a soft mass that may resemble the original tablet.

Manufactured for:
Janssen Pharmaceuticals, Inc.
Titusville, NJ 08560, USA

Licensed from Mitsubishi Tanabe Pharma Corporation

For patent information: www.janssenpatents.com

© Johnson & Johnson and its affiliates 2014 – 2024

Medication Guide
INVOKAMET®(in vok' a met)
(canagliflozin and metformin hydrochloride)
tablets, for oral use
and
INVOKAMET®(in vok' a met) XR
(canagliflozin and metformin hydrochloride)
extended-release tablets, for oral use

What is the most important information I should know about INVOKAMET or INVOKAMET XR?
INVOKAMET and INVOKAMET XR can cause serious side effects, including:

- Lactic Acidosis.Metformin, one of the medicines in INVOKAMET and INVOKAMET XR, can cause a rare but serious condition called lactic acidosis (a build-up of lactic acid in the blood) that can cause death. Lactic acidosis is a medical emergency and must be treated in the hospital.
  Stop taking INVOKAMET or INVOKAMET XR and call your healthcare provider right away if you have any of the following symptoms of lactic acidosis:

- feel cold in your hands or feet
- feel very weak or tired
- have trouble breathing
- have stomach pains, nausea, or vomiting

- have a slow or irregular heartbeat
- have unusual (not normal) muscle pain
- have unusual sleepiness or sleep longer than usual
- feel dizzy or lightheaded

Most people who have had lactic acidosis had other conditions that, in combination with metformin use, led to the lactic acidosis. Tell your healthcare provider if you have any of the following, because you have a higher chance for getting lactic acidosis with INVOKAMET or INVOKAMET XR if you:

- have severe kidney problems or your kidneys are affected by certain x-ray tests that use injectable dye.
- have liver problems.
- drink alcohol very often or drink a lot of alcohol in short-term "binge" drinking.
- get dehydrated (lose a large amount of body fluids). This can happen if you are sick with a fever, vomiting, or diarrhea. Dehydration can also happen when you sweat a lot with activity or exercise and do not drink enough fluids.
- have surgery.
- have new or worsening symptoms of congestive heart failure such as shortness of breath or increased fluid or swelling of the legs.
- have a heart attack, severe infection, or stroke.
- are 65 years of age or older.

The best way to keep from having a problem with lactic acidosis from metformin is to tell your healthcare provider if you have any of the problems in the list above. Your healthcare provider will decide to stop your INVOKAMET or INVOKAMET XR for a while if you have any of these things.

- Diabetic ketoacidosis (increased ketones in your blood or urine) in people with type 1 and other ketoacidosis.INVOKAMET and INVOKAMET XR can cause ketoacidosis that can be life-threatening and may lead to death. Ketoacidosis is a serious condition which needs to be treated in a hospital. People with type 1 diabetes have a high risk of getting ketoacidosis. People with type 2 diabetes or pancreas problems also have an increased risk of getting ketoacidosis. Ketoacidosis can also happen in people who: are sick, cannot eat or drink as usual, skip meals, are on a diet high in fat and low in carbohydrates (ketogenic diet), take less than the usual amount of insulin or miss insulin doses, drink too much alcohol, have a loss of too much fluid from the body (volume depletion), or who have surgery or a procedure that requires not having food for a long time (prolonged fasting). Ketoacidosis can happen even if your blood sugar is less than 250 mg/dL. Your health care provider may ask you to periodically check ketones in your urine or blood.
- Stop taking INVOKAMET or INVOKAMET XR and call your health care provider or get medical help right away if you get any of the following. If possible, check for ketones in your urine or blood, even if your blood sugar is less than 250 mg/dL:

- nausea
- vomiting
- stomach-area (abdominal) pain

- tiredness
- trouble breathing
- ketones in your urine or blood

- Amputations. INVOKAMET or INVOKAMET XR may increase your risk of lower limb amputations. Amputations mainly involve removal of the toe or part of the foot, however, amputations involving the leg, below and above the knee, have also occurred. Some people had more than one amputation, some on both sides of the body.
  You may be at a higher risk of lower limb amputation if you:
  - have a history of amputation
  - have heart disease or are at risk for heart disease
  - have had blocked or narrowed blood vessels, usually in your leg
  - have damage to the nerves (neuropathy) in your leg
  - have had diabetic foot ulcers or sores

Call your healthcare provider right away if you have new pain or tenderness, any sores, ulcers, or infections in your leg or foot.Your healthcare provider may decide to stop your INVOKAMET or INVOKAMET XR for a while if you have any of these signs or symptoms.

Talk to your healthcare provider about proper foot care.

- Dehydration.INVOKAMET or INVOKAMET XR can cause some people to become dehydrated (the loss of too much body water). Dehydration may cause you to feel dizzy, faint, lightheaded, or weak, especially when you stand up (orthostatic hypotension). There have been reports of sudden worsening of kidney function in people with type 2 diabetes who are taking canagliflozin, one of the medicines in INVOKAMET and INVOKAMET XR.
  You may be at higher risk of dehydration if you:
  - take medicines to lower your blood pressure, including diuretics (water pill)
  - are on a low sodium (salt) diet
  - have kidney problems
  - are 65 years of age or older

Talk to your healthcare provider about what you can do to prevent dehydration including how much fluid you should drink on a daily basis. Call your health care provider right away if you reduce the amount of food or liquid you drink, for example if you cannot eat or you start to lose liquids from your body, for example from vomiting, diarrhea, or being in the sun too long.

- Vaginal yeast infection.Women who take INVOKAMET or INVOKAMET XR may get vaginal yeast infections. Yeast infections can be a serious but common side effect of INVOKAMET or INVOKAMET XR. Symptoms of a vaginal yeast infection include:
  - vaginal odor
  - white or yellowish vaginal discharge (discharge may be lumpy or look like cottage cheese)
  - vaginal itching

- Yeast infection of the skin around the penis (balanitis or balanoposthitis).Men who take INVOKAMET or INVOKAMET XR may get a yeast infection of the skin around the penis. Men who are not circumcised may have swelling of the penis that makes it difficult to pull back the skin around the tip of the penis. Other symptoms of yeast infection of the penis include:

- redness, itching, or swelling of the penis
- foul smelling discharge from the penis

- rash of the penis
- pain in the skin around the penis

Talk to your healthcare provider about what to do if you get symptoms of a yeast infection of the vagina or penis. Your healthcare provider may suggest you use an over-the-counter antifungal medicine. Talk to your healthcare provider right away if you use an over-the-counter antifungal medication and your symptoms do not go away.

INVOKAMET or INVOKAMET XR can have other serious side effects.See " What are the possible side effects of INVOKAMET or INVOKAMET XR?"

What is INVOKAMET or INVOKAMET XR?

- INVOKAMET contains 2 prescription medicines called canagliflozin (INVOKANA) and metformin hydrochloride (HCl).
- INVOKAMET XR contains 2 prescription medicines called canagliflozin (INVOKANA) and metformin HCL extended- release.
- INVOKAMET or INVOKAMET XR can be used along with diet and exercise to lower blood sugar (glucose) in adults and children aged 10 years and older with type 2 diabetes.
  - One of the medicines in INVOKAMET or INVOKAMET XR, canagliflozin (INVOKANA), can also be used in adults with type 2 diabetes who have:
  - cardiovascular disease and canagliflozin is needed to reduce the risk of major cardiovascular events such as heart attack, stroke, or death.
  - diabetic kidney disease (nephropathy) with a certain amount of protein in the urine, and canagliflozin is needed to reduce the risk of end stage kidney disease (ESKD), worsening of kidney function, cardiovascular death, and hospitalization for heart failure.
- INVOKAMET or INVOKAMET XR is not used to lower blood sugar (glucose) in people with type 1 diabetes. It is not known if INVOKAMET or INVOKAMET XR is safe and effective in children under 10 years of age.

Do not take INVOKAMET or INVOKAMET XR if you:

- have severe kidney problems
- have a condition called metabolic acidosis, including diabetic ketoacidosis (increased ketones in the blood or urine).
- are allergic to canagliflozin, metformin, or any of the ingredients in INVOKAMET or INVOKAMET XR. See the end of this Medication Guide for a list of ingredients in INVOKAMET and INVOKAMET XR. Symptoms of an allergic reaction to INVOKAMET and INVOKAMET XR may include:
  - rash
  - raised red patches on your skin (hives)
  - swelling of the face, lips, mouth, tongue, and throat that may cause difficulty in breathing or swallowing

Before taking INVOKAMET or INVOKAMET XR, tell your healthcare provider about all of your medical conditions, including if you:

- have type 1 diabetes or have had diabetic ketoacidosis.
- have a decrease in your insulin dose.
- have a serious infection.
- have a history of infection of the vagina or penis.
- have a history of amputation.
- have had blocked or narrowed blood vessels, usually in your leg.
- have damage to the nerves (neuropathy) in your leg.
- have had diabetic foot ulcers or sores.
- have moderate to severe kidney problems.
- have liver problems.
- have a history of urinary tract infections or problems with urination.
- are on a low sodium (salt) diet. Your healthcare provider may change your diet or your dose of INVOKAMET or INVOKAMET XR.
- have ever had an allergic reaction to INVOKAMET or INVOKAMET XR.
- are going to get an injection of dye or contrast agents for an x-ray procedure. INVOKAMET or INVOKAMET XR may need to be stopped for a short time. Talk to your healthcare provider about when you should stop INVOKAMET or INVOKAMET XR and when you should start INVOKAMET or INVOKAMET XR again. See " What is the most important information I should know about INVOKAMET or INVOKAMET XR?"
- have heart problems, including congestive heart failure.
- are going to have surgery or a procedure that requires not having food for a long time (prolonged fasting). Your healthcare provider may stop your INVOKAMET or INVOKAMET XR before you have surgery. Talk to your healthcare provider if you are having surgery about when to stop taking INVOKAMET or INVOKAMET XR and when to start it again.
- are eating less or there is a change in your diet.
- are dehydrated.
- have or have had problems with your pancreas, including pancreatitis or surgery on your pancreas.
- drink alcohol very often or drink a lot of alcohol in the short-term ("binge" drinking).
- have low levels of vitamin B12or calcium in your blood.
- are pregnant or plan to become pregnant. INVOKAMET or INVOKAMET XR may harm your unborn baby. If you become pregnant while taking INVOKAMET or INVOKAMET XR, tell your healthcare provider as soon as possible. Talk with your healthcare provider about the best way to control your blood sugar while you are pregnant.
- are premenopausal (before the "change of life"), and do not have periods regularly or at all. INVOKAMET or INVOKAMET XR may increase your chance of becoming pregnant. Talk to your healthcare provider about birth control choices while taking INVOKAMET or INVOKAMET XR, if you are not planning to become pregnant. Tell your healthcare provider right away if you become pregnant while taking INVOKAMET or INVOKAMET XR.
- are breastfeeding or plan to breastfeed. INVOKAMET or INVOKAMET XR may pass into your breast milk and may harm your baby. Talk with your healthcare provider about the best way to feed your baby if you are taking INVOKAMET or INVOKAMET XR. Do not breastfeed while taking INVOKAMET or INVOKAMET XR.

Tell your healthcare provider about all the medicines you take,including prescription and over-the-counter medicines, vitamins, and herbal supplements.

INVOKAMET or INVOKAMET XR may affect the way other medicines work and other medicines may affect how INVOKAMET or INVOKAMET XR works. Know the medicines you take. Keep a list of them and show it to your healthcare provider and pharmacist when you get a new medicine.

How should I take INVOKAMET or INVOKAMET XR?

- If you are prescribed INVOKAMET, take by mouth 2 times each day with meals exactly as your healthcare provider tells you to take it. Taking INVOKAMET with meals may lower your chance of having an upset stomach.
- If you are prescribed INVOKAMET XR, take by mouth 1 time each day with the morning meal exactly as your healthcare provider tells you to take it. Taking INVOKAMET XR with a meal may lower your chance of having an upset stomach.
- Swallow INVOKAMET XR whole. Do not crush, cut, or chew.
- You may sometimes pass a soft mass in your stools (bowel movement) that looks like INVOKAMET XR tablets. It is normal to see this in your stool.
- Your healthcare provider may change your dose if needed.
- Your healthcare provider may tell you to take INVOKAMET or INVOKAMET XR along with other diabetes medicines. Low blood sugar can happen more often when INVOKAMET or INVOKAMET XR is taken with certain other diabetes medicines. See " What are the possible side effects of INVOKAMET or INVOKAMET XR?"
- Your healthcare provider may tell you to stop taking INVOKAMET or INVOKAMET XR at least 3 days before any surgery or procedure that requires not having food for a long time (prolonged fasting).
- If you miss a dose of INVOKAMET, take it as soon as you remember. If it is almost time for your next dose, skip the missed dose and take the medicine at the next regularly scheduled time. Do not take 2 tablets of INVOKAMET at the same time. Talk to your healthcare provider if you have questions about a missed dose.
- If you miss a dose of INVOKAMET XR, take it as soon as you remember. If it is almost time for your next dose, skip the missed dose and take the medicine at the next regularly scheduled time. Do not take more than 2 tablets of INVOKAMET XR at the same time. Talk to your healthcare provider if you have questions about a missed dose.
- If you take too much INVOKAMET or INVOKAMET XR, call your healthcare provider or Poison Help line at 1-800-222-1222 or go to the nearest hospital emergency room right away.
- When your body is under some types of stress, such as fever, trauma (such as a car accident), infection, or surgery, the amount of diabetes medicine you need may change. Tell your healthcare provider right away if you have any of these conditions and follow your healthcare provider's instructions.
- INVOKAMET and INVOKAMET XR will cause your urine to test positive for glucose.
- Your healthcare provider may do certain blood tests before you start INVOKAMET or INVOKAMET XR and during treatment as needed. Your healthcare provider may change your dose of INVOKAMET or INVOKAMET XR based on the results of your blood tests.

What should I avoid while taking INVOKAMET or INVOKAMET XR?

- Avoid drinking alcohol very often or drinking a lot of alcohol in a short period of time ("binge" drinking). It can increase your chances of getting serious side effects.

What are the possible side effects of INVOKAMET or INVOKAMET XR?

INVOKAMET or INVOKAMET XR may cause serious side effects including:

- See " What is the most important information I should know about INVOKAMET or INVOKAMET XR?"
- serious urinary tract infections.Serious urinary tract infections that may lead to hospitalization have happened in people who are taking canagliflozin, one of the medicines in INVOKAMET and INVOKAMET XR. Tell your healthcare provider if you have any signs or symptoms of a urinary tract infection such as a burning feeling when passing urine, a need to urinate often, the need to urinate right away, pain in the lower part of your stomach (pelvis), or blood in the urine. Sometimes people may also have a fever, back pain, nausea, or vomiting.
- low blood sugar (hypoglycemia).If you take INVOKAMET or INVOKAMET XR with another medicine that can cause low blood sugar, such as a sulfonylurea or insulin, your risk of getting low blood sugar is higher. The dose of your sulfonylurea medicine or insulin may need to be lowered while you take INVOKAMET or INVOKAMET XR. Signs and symptoms of low blood sugar may include:

- headache
- confusion
- hunger
- shaking or feeling jittery

- drowsiness
- dizziness
- fast heartbeat

- weakness
- irritability
- sweating

- a rare but serious bacterial infection that causes damage to the tissue under the skin (necrotizing fasciitis) in the area between and around the anus and genitals (perineum).Necrotizing fasciitis of the perineum has happened in people who take canagliflozin, one of the medicines in INVOKAMET and INVOKAMET XR. Necrotizing fasciitis of the perineum may lead to hospitalization, may require multiple surgeries, and may lead to death. Seek medical attention immediately if you have a fever or you are feeling very weak, tired or uncomfortable (malaise) and you develop any of the following symptoms in the area between and around your anus and genitals:

- pain or tenderness

- swelling

- redness of the skin (erythema)

- serious allergic reaction.If you have any symptoms of a serious allergic reaction, stop taking INVOKAMET or INVOKAMET XR and call your healthcare provider right away or go to the nearest hospital emergency room. See " Do not take INVOKAMET or INVOKAMET XR if you:". Your healthcare provider may give you a medicine for your allergic reaction and prescribe a different medicine for your diabetes.
- broken bones (fractures).Bone fractures have been seen in patients taking canagliflozin. Talk to your healthcare provider about factors that may increase your risk of bone fracture.
- low vitamin B12(vitamin B12deficiency). Using metformin for long periods of time may cause a decrease in the amount of vitamin B12in your blood, especially if you have had low vitamin B12blood levels before. Your healthcare provider may order blood tests to check your vitamin B12levels.

Other common side effects of INVOKAMET or INVOKAMET XR include:

- nausea and vomiting
- gas

- diarrhea
- upset stomach

- weakness
- indigestion

- headache

- changes in urination, including urgent need to urinate more often, in larger amounts, or at night

These are not all the possible side effects of INVOKAMET or INVOKAMET XR.

Call your doctor for medical advice about side effects. You may report side effects to FDA at 1-800-FDA-1088.

You may also report side effects to Janssen Pharmaceuticals, Inc. at 1-800-526-7736.

How should I store INVOKAMET or INVOKAMET XR?

- Store INVOKAMET or INVOKAMET XR at room temperature between 68 °F to 77 °F (20 °C to 25 °C).
- Store INVOKAMET or INVOKAMET XR in the original container to protect from moisture. Storage in a pill box or pill organizer is allowed for up to 30 days.

Keep INVOKAMET and INVOKAMET XR and all medicines out of the reach of children.

General information about the safe and effective use of INVOKAMET or INVOKAMET XR.

Medicines are sometimes prescribed for purposes other than those listed in a Medication Guide. Do not use INVOKAMET or INVOKAMET XR for a condition for which it was not prescribed. Do not give INVOKAMET or INVOKAMET XR to other people, even if they have the same symptoms that you have. It may harm them.

You can ask your pharmacist or healthcare provider for information about INVOKAMET or INVOKAMET XR that is written for health professionals.

What are the ingredients in INVOKAMET?

Active ingredients: canagliflozin and metformin HCl

Inactive ingredients: The tablet core contains croscarmellose sodium (E468), hypromellose, magnesium stearate (E572), and microcrystalline cellulose (E460[i]). The magnesium stearate is vegetable-sourced. In addition, the tablet coating contains Macrogol/PEG3350 (E1521), polyvinyl alcohol (E1203) (partially hydrolyzed), talc (E553b), titanium dioxide (E171), iron oxide yellow (E172) (50 mg/1,000 mg and 150 mg/500 mg tablets only), iron oxide red (E172) (50 mg/1,000 mg, 150 mg/500 mg and 150 mg/1,000 mg tablets only), and iron oxide black (E172) (150 mg/1,000 mg tablets only).

What are the ingredients of INVOKAMET XR?

Active ingredients: canagliflozin and metformin HCl

Inactive ingredients: The tablet core contains croscarmellose sodium (E468), hydroxypropyl cellulose (E463), hypromellose, lactose anhydrous, magnesium stearate (E572) (vegetable-sourced), microcrystalline cellulose (E460[i]), polyethylene oxide, and silicified microcrystalline cellulose (50 mg/500 mg and 50 mg/1,000 mg tablets only). In addition, the tablet coating contains macrogol/PEG3350 (E1521), polyvinyl alcohol (E1203) (partially hydrolyzed), talc (E553b), titanium dioxide (E171), iron oxide red (E172), iron oxide yellow (E172), and iron oxide black (E172) (50 mg/1,000 mg and 150 mg/1,000 mg tablets only).

Manufactured for: Janssen Pharmaceuticals, Inc., Titusville, NJ 08560, USA. Licensed from Mitsubishi Tanabe Pharma Corporation. For patent information: www.janssenpatents.com © Johnson & Johnson and its affiliates 2014 – 2024

For more information about INVOKAMET or INVOKAMET XR, call 1-800-526-7736 or visit our websites at www.invokamet.com or www.invokametxr.com.

This Medication Guide has been approved by the U.S. Food and Drug Administration.

Revised: 12/2024

PRINCIPAL DISPLAY PANEL - 50 mg/500 mg Tablet Bottle Label - 540

NDC 50458-540-60
60 tablets

Invokamet®
(canagliflozin and
metformin HCl)
Tablets 50 mg/500 mg

Dispense with Medication Guide

Store and Dispense in the original container.
May be stored in a pill box for up to 30 days.

janssen

Rx only

PRINCIPAL DISPLAY PANEL - 50 mg/1,000 mg Tablet Bottle Label - 541

NDC 50458-541-60
60 tablets

Invokamet®
(canagliflozin and
metformin HCl)
Tablets 50 mg/1,000 mg

Dispense with Medication Guide

Store and Dispense in the original container.

May be stored in a pill box for up to 30 days.

janssen

Rx only

PRINCIPAL DISPLAY PANEL - 150 mg/500 mg Tablet Bottle Label - 542

NDC 50458-542-60
60 tablets

Invokamet®
(canagliflozin and
metformin HCl)
Tablets 150 mg/500 mg

Dispense with Medication Guide

Store and Dispense in the original container.

May be stored in a pill box for up to 30 days.

janssen

Rx only

PRINCIPAL DISPLAY PANEL - 150 mg/1,000 mg Tablet Bottle Label - 543

NDC 50458-543-60
60 tablets

Invokamet®
(canagliflozin and
metformin HCl)
Tablets 150 mg/1,000 mg

Dispense with Medication Guide

Store and Dispense in the original container.

May be stored in a pill box for up to 30 days.

janssen

Rx only

PRINCIPAL DISPLAY PANEL - 50 mg/500 mg Tablet Bottle Label - 940

NDC 50458-940-01
60 tablets

Invokamet®XR
(canagliflozin and metformin HCl
extended-release) tablets

50 mg/500 mg

Dispense with Medication Guide

Store and Dispense in the original
container.

May be stored in a pill box
for up to 30 days.

janssen

Rx only

PRINCIPAL DISPLAY PANEL - 50 mg/1000 mg Tablet Bottle Label - 941

NDC 50458-941-01
60 tablets

Invokamet®XR
(canagliflozin and metformin HCl
extended-release) tablets

50 mg/1000 mg

Dispense with Medication Guide

Store and Dispense in the original
container.

May be stored in a pill box
for up to 30 days.

janssen

Rx only

PRINCIPAL DISPLAY PANEL - 150 mg/500 mg Tablet Bottle Label - 942

NDC 50458-942-01
60 tablets

Invokamet®XR
(canagliflozin and metformin HCl
extended-release) tablets

150 mg/500 mg

Dispense with Medication Guide

Store and Dispense in the original
container.

May be stored in a pill box
for up to 30 days.

janssen

Rx only

PRINCIPAL DISPLAY PANEL - 150 mg/1000 mg Tablet Bottle Label - 943

NDC 50458-943-01
60 tablets

Invokamet®XR
(canagliflozin and metformin HCl
extended-release) tablets

150 mg/1000 mg

Dispense with Medication Guide

Store and Dispense in the original
container.

May be stored in a pill box
for up to 30 days.

janssen

Rx only